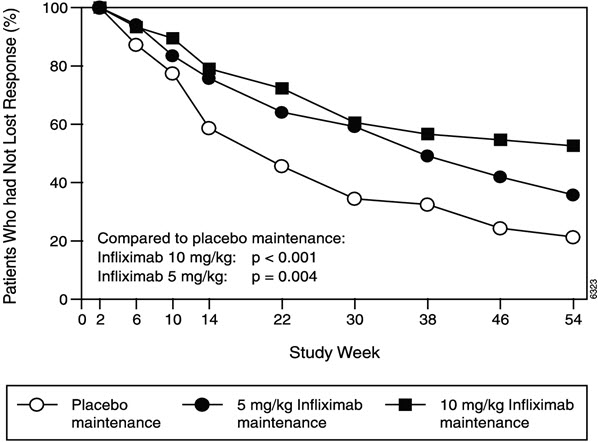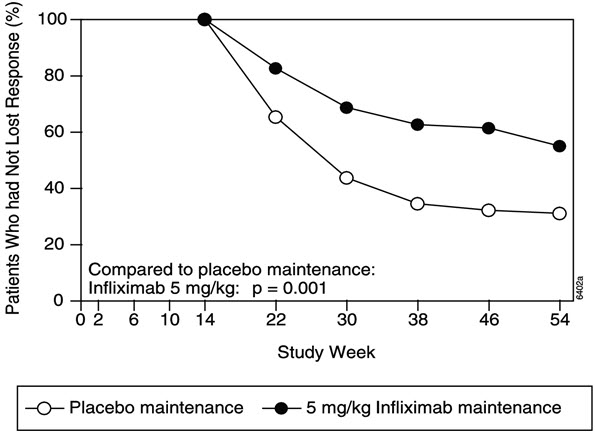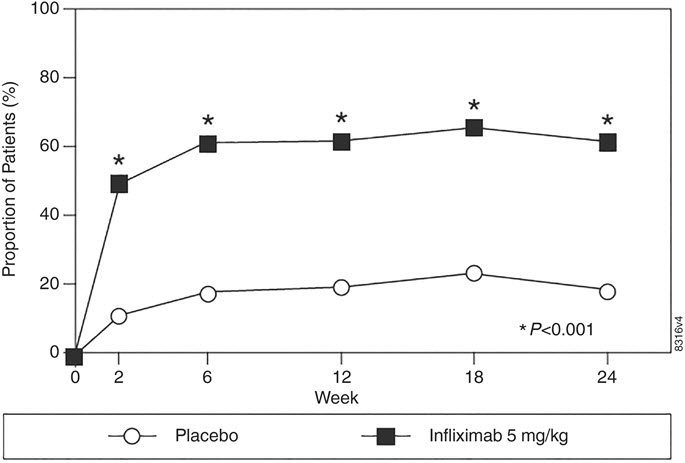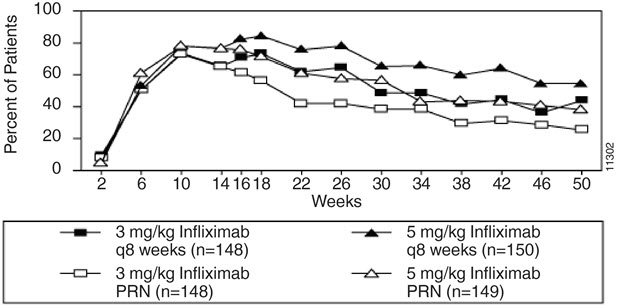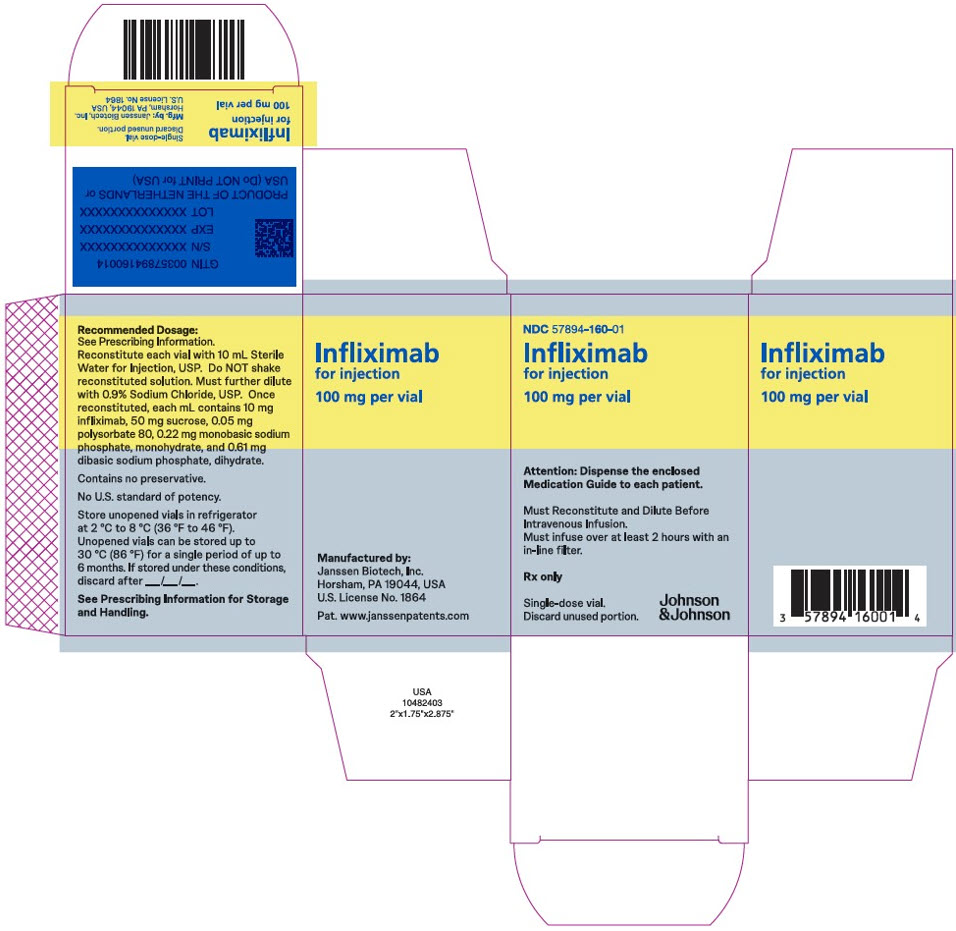 DRUG LABEL: INFLIXIMAB
NDC: 57894-160 | Form: INJECTION, POWDER, LYOPHILIZED, FOR SOLUTION
Manufacturer: Janssen Biotech, Inc.
Category: prescription | Type: HUMAN PRESCRIPTION DRUG LABEL
Date: 20260211

ACTIVE INGREDIENTS: INFLIXIMAB 100 mg/10 mL
INACTIVE INGREDIENTS: SUCROSE 500 mg/10 mL; POLYSORBATE 80 0.5 mg/10 mL; SODIUM PHOSPHATE, MONOBASIC, MONOHYDRATE 2.2 mg/10 mL; SODIUM PHOSPHATE, DIBASIC, DIHYDRATE 6.1 mg/10 mL

HIGHLIGHTS OF PRESCRIBING INFORMATION

These highlights do not include all the information needed to use INFLIXIMAB safely and effectively. See full prescribing information for INFLIXIMAB.
INFLIXIMAB for injection, for intravenous use
Initial U.S. Approval: 1998

WARNING: SERIOUS INFECTIONS and MALIGNANCY

See full prescribing information for complete boxed warning.

- Increased risk of serious infections leading to hospitalization or death, including tuberculosis (TB), bacterial sepsis, invasive fungal infections (such as histoplasmosis) and infections due to other opportunistic pathogens. (5.1)
- Discontinue Infliximab if a patient develops a serious infection.
- Perform test for latent TB; if positive, start treatment for TB prior to starting Infliximab. Monitor all patients for active TB during treatment, even if initial latent TB test is negative. (5.1)
- Lymphoma and other malignancies, some fatal, have been reported in children and adolescent patients treated with tumor necrosis factor (TNF) blockers, including Infliximab. (5.2)
- Postmarketing cases of fatal hepatosplenic T-cell lymphoma (HSTCL) have been reported in patients treated with TNF blockers including Infliximab. Almost all had received azathioprine or 6-mercaptopurine concomitantly with a TNF blocker at or prior to diagnosis. The majority of Infliximab cases were reported in patients with Crohn's disease or ulcerative colitis, most of whom were adolescent or young adult males. (5.2)

1 INDICATIONS AND USAGE

Infliximab is a tumor necrosis factor (TNF) blocker indicated for:

- Crohn's Disease:
  - reducing signs and symptoms and inducing and maintaining clinical remission in adult patients with moderately to severely active disease who have had an inadequate response to conventional therapy. (1.1)
  - reducing the number of draining enterocutaneous and rectovaginal fistulas and maintaining fistula closure in adult patients with fistulizing disease. (1.1)
- Pediatric Crohn's Disease: reducing signs and symptoms and inducing and maintaining clinical remission in pediatric patients 6 years of age and older with moderately to severely active disease who have had an inadequate response to conventional therapy. (1.2)
- Ulcerative Colitis: reducing signs and symptoms, inducing and maintaining clinical remission and mucosal healing, and eliminating corticosteroid use in adult patients with moderately to severely active disease who have had an inadequate response to conventional therapy. (1.3)
- Pediatric Ulcerative Colitis: reducing signs and symptoms and inducing and maintaining clinical remission in pediatric patients 6 years of age and older with moderately to severely active disease who have had an inadequate response to conventional therapy. (1.4)
- Rheumatoid Arthritis in combination with methotrexate: reducing signs and symptoms, inhibiting the progression of structural damage, and improving physical function in adult patients with moderately to severely active disease. (1.5)
- Ankylosing Spondylitis: reducing signs and symptoms in adult patients with active disease. (1.6)
- Psoriatic Arthritis: reducing signs and symptoms of active arthritis, inhibiting the progression of structural damage, and improving physical function in adult patients. (1.7)
- Plaque Psoriasis: treatment of adult patients with chronic severe (i.e., extensive and/or disabling) plaque psoriasis who are candidates for systemic therapy and when other systemic therapies are medically less appropriate. (1.8)

2 DOSAGE AND ADMINISTRATION

- Prior to treatment, ensure appropriate personnel and medication are available to treat reactions (e.g., hypersensitivity) that occur during infusion and shortly after infusion. (2.11)
- Infliximab is administered by intravenous infusion for at least 2 hours with an in-line filter (2.11)
- Crohn's Disease: 5 mg/kg at 0, 2 and 6 weeks, then every 8 weeks. Some adult patients who initially respond to treatment may benefit from increasing the dose to 10 mg/kg every 8 weeks if they later lose their response. (2.1)
- Pediatric Crohn's Disease (≥ 6 years old): 5 mg/kg at 0, 2 and 6 weeks, then every 8 weeks. (2.2)
- Ulcerative Colitis: 5 mg/kg at 0, 2 and 6 weeks, then every 8 weeks. (2.3)
- Pediatric Ulcerative Colitis (≥ 6 years old): 5 mg/kg at 0, 2 and 6 weeks, then every 8 weeks. (2.4)
- Rheumatoid Arthritis: In conjunction with methotrexate, 3 mg/kg at 0, 2 and 6 weeks, then every 8 weeks. Some patients may benefit from increasing the dose up to 10 mg/kg every 8 weeks or treating as often as every 4 weeks. (2.5)
- Ankylosing Spondylitis: 5 mg/kg at 0, 2 and 6 weeks, then every 6 weeks. (2.6)
- Psoriatic Arthritisand Plaque Psoriasis: 5 mg/kg at 0, 2 and 6 weeks, then every 8 weeks. (2.7, 2.8)

3 DOSAGE FORMS AND STRENGTHS

For injection: 100 mg of infliximab as a lyophilized powder in a single-dose vial for reconstitution and dilution. (2.11, 3)

4 CONTRAINDICATIONS

- Infliximab doses >5 mg/kg in moderate or severe heart failure. (4)
- Previous severe hypersensitivity reaction to infliximab or any inactive ingredients of Infliximab or to any murine proteins. (4)

5 WARNINGS AND PRECAUTIONS

- Serious infections– do not give Infliximab during an active infection. If an infection develops, monitor carefully and stop Infliximab if infection becomes serious. (5.1)
- Invasive fungal infections– for patients who develop a systemic illness on Infliximab, consider empiric antifungal therapy for those who reside or travel to regions where mycoses are endemic (5.1)
- Malignancies– the incidence of malignancies, including invasive cervical cancer and lymphoma, was greater in Infliximab treated patients than in controls. Due to the risk of HSTCL carefully assess the risk/benefit especially if the patient has Crohn's disease or ulcerative colitis, is male, and is receiving azathioprine or 6-mercaptopurine treatment. (5.2)
- Hepatitis B virus reactivation– test for HBV infection before starting Infliximab. Monitor HBV carriers during and several months after therapy. If reactivation occurs, stop Infliximab and begin anti-viral therapy. (5.3)
- Hepatotoxicity– severe hepatic reactions, some fatal or necessitating liver transplantation. Stop Infliximab in cases of jaundice and/or marked liver enzyme elevations. (5.4)
- Heart failure– new onset or worsening symptoms may occur. (4, 5.5)
- Cytopenias– advise patients to seek immediate medical attention if signs and symptoms develop, and consider stopping Infliximab. (5.6)
- Hypersensitivity– serious infusion reactions including anaphylaxis or serum sickness-like reactions may occur. (5.7)
- Cardiovascular and Cerebrovascular Reactions– Cerebrovascular accidents, myocardial infarctions (some fatal), and arrhythmias have been reported during and within 24 hours of initiation of Infliximab infusion. Monitor patients during Infliximab infusion and if serious reaction occurs, discontinue infusion. (5.8)
- Demyelinating disease– exacerbation or new onset may occur. (5.9)
- Lupus-like syndrome– stop Infliximab if syndrome develops. (5.12)
- Vaccinations and Use of Live Vaccines/Therapeutic Infectious Agents– Prior to initiating Infliximab bring pediatric and adult patients up to date with all vaccinations. Live vaccines or therapeutic infectious agents should not be given with Infliximab. At least a six month waiting period following birth is recommended before the administration of live vaccines to infants exposed in uteroto infliximab (5.13).

6 ADVERSE REACTIONS

Most common adverse reactions (>10%) – infections (e.g. upper respiratory, sinusitis, and pharyngitis), infusion-related reactions, headache, and abdominal pain. (6.1)

To report SUSPECTED ADVERSE REACTIONS, contact Janssen Biotech, Inc. at 1-800-526-7736 or FDA at 1-800-FDA-1088 or www.fda.gov/medwatch.

7 DRUG INTERACTIONS

Other Biological Products– increased risk of serious infections. (7.1)

FULL PRESCRIBING INFORMATION

WARNING: SERIOUS INFECTIONS and MALIGNANCY

SERIOUS INFECTIONS

Patients treated with Infliximab are at increased risk for developing serious infections that may lead to hospitalization or death [see Warnings and Precautions (5.1)and Adverse Reactions (6.1)] . Most patients who developed these infections were taking concomitant immunosuppressants such as methotrexate or corticosteroids.

Infliximab should be discontinued if a patient develops a serious infection or sepsis.

Reported infections include:

- Active tuberculosis, including reactivation of latent tuberculosis. Patients with tuberculosis have frequently presented with disseminated or extrapulmonary disease. Patients should be tested for latent tuberculosis before Infliximab use and during therapy. Treatment for latent infection should be initiated prior to Infliximab use.
- Invasive fungal infections, including histoplasmosis, coccidioidomycosis, candidiasis, aspergillosis, blastomycosis, and pneumocystosis. Patients with histoplasmosis or other invasive fungal infections may present with disseminated, rather than localized, disease. Antigen and antibody testing for histoplasmosis may be negative in some patients with active infection. Empiric anti-fungal therapy should be considered in patients at risk for invasive fungal infections who develop severe systemic illness.
- Bacterial, viral and other infections due to opportunistic pathogens, including Legionella and Listeria.

The risks and benefits of treatment with Infliximab should be carefully considered prior to initiating therapy in patients with chronic or recurrent infection.

Patients should be closely monitored for the development of signs and symptoms of infection during and after treatment with Infliximab, including the possible development of tuberculosis in patients who tested negative for latent tuberculosis infection prior to initiating therapy.

MALIGNANCY

Lymphoma and other malignancies, some fatal, have been reported in children and adolescent patients treated with TNF blockers, including Infliximab [see Warnings and Precautions (5.2)] .

Postmarketing cases of hepatosplenic T-cell lymphoma (HSTCL), a rare type of T-cell lymphoma, have been reported in patients treated with TNF blockers including Infliximab. These cases have had a very aggressive disease course and have been fatal. Almost all patients had received treatment with azathioprine or 6-mercaptopurine concomitantly with a TNF blocker at or prior to diagnosis. The majority of reported Infliximab cases have occurred in patients with Crohn's disease or ulcerative colitis and most were in adolescent and young adult males.

1 INDICATIONS AND USAGE

1.1 Crohn's Disease

Infliximab is indicated for:

- reducing signs and symptoms and inducing and maintaining clinical remission in adult patients with moderately to severely active Crohn's disease (CD) who have had an inadequate response to conventional therapy.
- reducing the number of draining enterocutaneous and rectovaginal fistulas and maintaining fistula closure in adult patients with fistulizing CD.

1.2 Pediatric Crohn's Disease

Infliximab is indicated for reducing signs and symptoms and inducing and maintaining clinical remission in pediatric patients 6 years of age and older with moderately to severely active CD who have had an inadequate response to conventional therapy.

1.3 Ulcerative Colitis

Infliximab is indicated for reducing signs and symptoms, inducing and maintaining clinical remission and mucosal healing, and eliminating corticosteroid use in adult patients with moderately to severely active ulcerative colitis (UC) who have had an inadequate response to conventional therapy.

1.4 Pediatric Ulcerative Colitis

Infliximab is indicated for reducing signs and symptoms and inducing and maintaining clinical remission in pediatric patients 6 years of age and older with moderately to severely active UC who have had an inadequate response to conventional therapy.

1.5 Rheumatoid Arthritis

Infliximab, in combination with methotrexate, is indicated for reducing signs and symptoms, inhibiting the progression of structural damage, and improving physical function in adult patients with moderately to severely active rheumatoid arthritis (RA).

1.6 Ankylosing Spondylitis

Infliximab is indicated for reducing signs and symptoms in adult patients with active ankylosing spondylitis (AS).

1.7 Psoriatic Arthritis

Infliximab is indicated for reducing signs and symptoms of active arthritis, inhibiting the progression of structural damage, and improving physical function in adult patients with psoriatic arthritis (PsA).

1.8 Plaque Psoriasis

Infliximab is indicated for the treatment of adult patients with chronic severe (i.e., extensive and/or disabling) plaque psoriasis (Ps) who are candidates for systemic therapy and when other systemic therapies are medically less appropriate. Infliximab should only be administered to patients who will be closely monitored and have regular follow-up visits with a physician [see Boxed Warningand Warnings and Precautions (5)] .

2 DOSAGE AND ADMINISTRATION

2.1 Dosage in Adult Crohn's Disease

The recommended dosage of Infliximab is 5 mg/kg given as an intravenous induction regimen at 0, 2 and 6 weeks followed by a maintenance regimen of 5 mg/kg every 8 weeks thereafter for the treatment of adults with moderately to severely active CD or fistulizing CD. For adult patients who respond and then lose their response, consideration may be given to treatment with 10 mg/kg every 8 weeks. Patients who do not respond by Week 14 are unlikely to respond with continued dosing and consideration should be given to discontinue Infliximab in these patients.

2.2 Dosage in Pediatric Crohn's Disease

The recommended dosage of Infliximab for pediatric patients 6 years and older with moderately to severely active CD is 5 mg/kg given as an intravenous induction regimen at 0, 2 and 6 weeks followed by a maintenance regimen of 5 mg/kg every 8 weeks.

2.3 Dosage in Adult Ulcerative Colitis

The recommended dosage of Infliximab is 5 mg/kg given as an intravenous induction regimen at 0, 2 and 6 weeks followed by a maintenance regimen of 5 mg/kg every 8 weeks thereafter for the treatment of adult patients with moderately to severely active UC.

2.4 Dosage in Pediatric Ulcerative Colitis

The recommended dosage of Infliximab for pediatric patients 6 years and older with moderately to severely active UC is 5 mg/kg given as an intravenous induction regimen at 0, 2 and 6 weeks followed by a maintenance regimen of 5 mg/kg every 8 weeks.

2.5 Dosage in Rheumatoid Arthritis

The recommended dosage of Infliximab is 3 mg/kg given as an intravenous induction regimen at 0, 2 and 6 weeks followed by a maintenance regimen of 3 mg/kg every 8 weeks thereafter for the treatment of moderately to severely active RA. Infliximab should be given in combination with methotrexate. For patients who have an incomplete response, consideration may be given to adjusting the dosage up to 10 mg/kg every 8 weeks or treating as often as every 4 weeks bearing in mind that risk of serious infections is increased at higher doses per infusion or more frequent dosing [see Adverse Reactions (6.1)] .

2.6 Dosage in Ankylosing Spondylitis

The recommended dosage of Infliximab is 5 mg/kg given as an intravenous induction regimen at 0, 2 and 6 weeks followed by a maintenance regimen of 5 mg/kg every 6 weeks thereafter for the treatment of active AS.

2.7 Dosage in Psoriatic Arthritis

The recommended dosage of Infliximab is 5 mg/kg given as an intravenous induction regimen at 0, 2 and 6 weeks followed by a maintenance regimen of 5 mg/kg every 8 weeks thereafter for the treatment of PsA. Infliximab can be used with or without methotrexate.

2.8 Dosage in Plaque Psoriasis

The recommended dosage of Infliximab in adult patients is 5 mg/kg given as an intravenous induction regimen at 0, 2 and 6 weeks followed by a maintenance regimen of 5 mg/kg every 8 weeks thereafter for the treatment of chronic severe (i.e., extensive and/or disabling) Ps.

2.9 Assessment for Latent and Active Tuberculosis

Prior to initiating Infliximab and periodically during therapy, patients should be evaluated for active tuberculosis and tested for latent infection [see Warnings and Precautions (5.1)] .

2.10 Administration Instructions Regarding Infusion Reactions

Prior to treatment, ensure appropriate personnel and medication are available to treat reactions (e.g., hypersensitivity, other reactions) that occur during infusion and shortly after infusion. Prior to infusion with Infliximab, patients may be premedicated with histamine-1 receptor antagonists, histamine-2 receptor antagonists, acetaminophen, and/or corticosteroids [see Warnings and Precautions (5.7)] .

For mild to moderate reactions during the infusion, consider slowing or stopping the infusion. Upon resolution of these reactions, may reinitiate at a lower infusion rate and/or with histamine-1 receptor antagonists, histamine-2 receptor antagonists, acetaminophen, and/or corticosteroids. Discontinue the infusion if the mild to moderate reactions reoccur.

Discontinue the infusion if severe hypersensitivity reactions occur during the infusion.

2.11 Reconstitution, Dilution, and Administration Instructions

Infliximab is intended for use under the guidance and supervision of a healthcare provider. The supplied lyophilized powder must be reconstituted and diluted prior to administration. The infusion solution should be prepared and administered by a trained medical professional using aseptic technique by the following procedure:

1. Calculate the dose, total volume of reconstituted Infliximab solution required and the number of Infliximab vials needed. More than one vial may be needed for a full dose.
2. Reconstitute each 100 mg Infliximab vial with 10 mL of Sterile Water for Injection, USP, to obtain a concentration of 10 mg/mL, using a syringe equipped with a 21-gauge or smaller needle as follows:
  - Remove the flip-top from the vial and wipe the top with an alcohol swab.
  - Insert the syringe needle into the vial through the center of the rubber stopper and direct the stream of Sterile Water for Injection, USP, to the glass wall of the vial. Gently swirl the solution by rotating the vial to dissolve the lyophilized powder, which has a cake-like appearance. Avoid prolonged or vigorous agitation. DO NOT SHAKE. Foaming of the solution on reconstitution is not unusual.
  - Allow the reconstituted solution to stand for 5 minutes. Visually inspect the reconstituted solution for particulate matter and discoloration. The reconstituted solution should be colorless to light yellow and opalescent, and the solution may develop a few translucent particles as infliximab is a protein. Do not use if the lyophilized powder has not fully dissolved or if opaque particles, discoloration, or other foreign particles are present. Do not store unused reconstituted Infliximab solution.
3. Dilute the total volume of the reconstituted Infliximab solution to 250 mL [For volumes greater than 250 mL, either use a larger infusion bag (e.g. 500 mL) or multiple 250 mL infusion bags to ensure that the concentration of the infusion solution does not exceed 4 mg/mL.] with sterile 0.9% Sodium Chloride Injection, USP, (do not dilute with any other diluent) as follows:
  - Withdraw a volume from the 0.9% Sodium Chloride Injection, USP, 250 mL bottle or bag equal to the totalvolume of reconstituted Infliximab required for a dose. Slowly add the total volume of reconstituted Infliximab solution from the vial(s) to the 250 mL infusion bottle or bag.
  - Discard any unused portion of the reconstituted Infliximab solution remaining in the vial(s).
  - Gently invert the bag to mix the solution. The resulting infusion concentration should range between 0.4 mg/mL (minimum recommended concentration) and 4 mg/mL (maximum recommended concentration) of infliximab.
4. The Infliximab infusion should begin within 3 hours of reconstitution and dilution. The infusion must be administered intravenously for at least 2 hours with an infusion set with an in-line, sterile, non-pyrogenic, low-protein-binding filter (pore size of 1.2 µm or less).
5. Given that the vials do not contain antibacterial preservatives, discard any unused portion of the infusion solution (do not store for reuse).

No physical biochemical compatibility studies have been conducted to evaluate the co-administration of Infliximab with other agents. Infliximab should not be infused concomitantly in the same intravenous line with other agents.

3 DOSAGE FORMS AND STRENGTHS

For injection: 100 mg of infliximab as a white lyophilized powder in a single-dose vial for reconstitution and dilution.

4 CONTRAINDICATIONS

The use of Infliximab at doses >5 mg/kg is contraindicated in patients with moderate or severe heart failure [see Warnings and Precautions (5.5)and Adverse Reactions (6.1)] .

Infliximab is contraindicated in patients with a previous severe hypersensitivity reaction to infliximab or any of the inactive ingredients of Infliximab or any murine proteins [severe hypersensitivity reactions have included anaphylaxis, hypotension, and serum sickness] [see Warnings and Precautions (5.7)and Adverse Reactions (6.1)].

5 WARNINGS AND PRECAUTIONS

5.1 Serious Infections

Patients treated with Infliximab are at increased risk for developing serious infections involving various organ systems and sites that may lead to hospitalization or death.

Opportunistic infections due to bacterial, mycobacterial, invasive fungal, viral, or parasitic organisms including aspergillosis, blastomycosis, candidiasis, coccidioidomycosis, cryptococcosis, histoplasmosis, legionellosis, listeriosis, pneumocystosis, salmonellosis and tuberculosis have been reported with TNF blockers. Patients have frequently presented with disseminated rather than localized disease.

Treatment with Infliximab should not be initiated in patients with an active infection, including clinically important localized infections. Patients greater than 65 years of age, patients with co-morbid conditions and/or patients taking concomitant immunosuppressants such as corticosteroids or methotrexate may be at greater risk of infection. The risks and benefits of treatment should be considered prior to initiating therapy in patients:

- with chronic or recurrent infection;
- who have been exposed to tuberculosis;
- with a history of an opportunistic infection;
- who have resided or traveled in areas of endemic tuberculosis or endemic mycoses, such as histoplasmosis, coccidioidomycosis, or blastomycosis; or
- with underlying conditions that may predispose them to infection.

Tuberculosis

Cases of reactivation of tuberculosis or new tuberculosis infections have been observed in patients receiving Infliximab, including patients who have previously received treatment for latent or active tuberculosis. Cases of active tuberculosis have also occurred in patients being treated with Infliximab during treatment for latent tuberculosis.

Patients should be evaluated for tuberculosis risk factors and tested for latent infection prior to initiating Infliximab and periodically during therapy. Treatment of latent tuberculosis infection prior to therapy with TNF blockers has been shown to reduce the risk of tuberculosis reactivation during therapy. Induration of 5 mm or greater with tuberculin skin testing should be considered a positive test result when assessing if treatment for latent tuberculosis is needed prior to initiating Infliximab, even for patients previously vaccinated with Bacille Calmette-Guérin (BCG).

Anti-tuberculosis therapy should also be considered prior to initiation of Infliximab in patients with a past history of latent or active tuberculosis in whom an adequate course of treatment cannot be confirmed, and for patients with a negative test for latent tuberculosis but having risk factors for tuberculosis infection. Consultation with a physician with expertise in the treatment of tuberculosis is recommended to aid in the decision whether initiating anti-tuberculosis therapy is appropriate for an individual patient.

Tuberculosis should be strongly considered in patients who develop a new infection during Infliximab treatment, especially in patients who have previously or recently traveled to countries with a high prevalence of tuberculosis, or who have had close contact with a person with active tuberculosis.

Monitoring

Patients should be closely monitored for the development of signs and symptoms of infection during and after treatment with Infliximab, including the development of tuberculosis in patients who tested negative for latent tuberculosis infection prior to initiating therapy. Tests for latent tuberculosis infection may also be falsely negative while on therapy with Infliximab.

Infliximab should be discontinued if a patient develops a serious infection or sepsis. A patient who develops a new infection during treatment with Infliximab should be closely monitored, undergo a prompt and complete diagnostic workup appropriate for an immunocompromised patient, and appropriate antimicrobial therapy should be initiated.

Invasive Fungal Infections

For patients who reside or travel in regions where mycoses are endemic, invasive fungal infection should be suspected if they develop a serious systemic illness. Appropriate empiric antifungal therapy should be considered while a diagnostic workup is being performed. Antigen and antibody testing for histoplasmosis may be negative in some patients with active infection. When feasible, the decision to administer empiric antifungal therapy in these patients should be made in consultation with a physician with expertise in the diagnosis and treatment of invasive fungal infections and should take into account both the risk for severe fungal infection and the risks of antifungal therapy.

5.2 Malignancies

Malignancies, some fatal, have been reported among children, adolescents and young adults who received treatment with TNF blockers (initiation of therapy ≤18 years of age), including Infliximab. Approximately half of these cases were lymphomas, including Hodgkin's and non-Hodgkin's lymphoma. The other cases represented a variety of malignancies, including rare malignancies that are usually associated with immunosuppression and malignancies that are not usually observed in children and adolescents. The malignancies occurred after a median of 30 months (range 1 to 84 months) after the first dose of TNF blocker therapy. Most of the patients were receiving concomitant immunosuppressants. These cases were reported post-marketing and are derived from a variety of sources, including registries and spontaneous postmarketing reports.

Lymphomas

In the controlled portions of clinical trials of all the TNF blockers, more cases of lymphoma have been observed among patients receiving a TNF blocker compared with control patients. In the controlled and open-label portions of Infliximab clinical trials, 5 patients developed lymphomas among 5707 patients treated with Infliximab (median duration of follow-up 1.0 years) vs. 0 lymphomas in 1600 control patients (median duration of follow-up 0.4 years). In RA patients, 2 lymphomas were observed for a rate of 0.08 cases per 100 patient-years of follow-up, which is approximately three-fold higher than expected in the general population. In the combined clinical trial population for RA, CD, PsA, AS, UC, and Ps, 5 lymphomas were observed for a rate of 0.10 cases per 100 patient-years of follow-up, which is approximately four-fold higher than expected in the general population. Patients with CD, RA or Ps, particularly patients with highly active disease and/or chronic exposure to immunosuppressant therapies, may be at a higher risk (up to several fold) than the general population for the development of lymphoma, even in the absence of TNF blockers. Cases of acute and chronic leukemia have been reported with postmarketing TNF blocker use in RA and other diseases. Even in the absence of TNF blocker therapy, patients with RA may be at a higher risk (approximately 2-fold) than the general population for the development of leukemia.

Hepatosplenic T-cell Lymphoma (HSTCL)

Postmarketing cases of hepatosplenic T-cell lymphoma (HSTCL), a rare type of T-cell lymphoma, have been reported in patients treated with TNF blockers including Infliximab. These cases have had a very aggressive disease course and have been fatal. Almost all patients had received treatment with the immunosuppressants azathioprine or 6-mercaptopurine concomitantly with a TNF blocker at or prior to diagnosis. The majority of reported Infliximab cases have occurred in patients with CD or UC and most were in adolescent and young adult males. It is uncertain whether the occurrence of HSTCL is related to TNF blockers or TNF blockers in combination with these other immunosuppressants. When treating patients, consideration of whether to use Infliximab alone or in combination with other immunosuppressants such as azathioprine or 6-mercaptopurine should take into account a possibility that there is a higher risk of HSTCL with combination therapy versus an observed increased risk of immunogenicity and hypersensitivity reactions with Infliximab monotherapy from the clinical trial data [see Warnings and Precautions (5.7)and Adverse Reactions (6.1)] .

Skin Cancer

Melanoma and Merkel cell carcinoma have been reported in patients treated with TNF blocker therapy, including Infliximab [see Adverse Reactions (6.3)] . Periodic skin examination is recommended for all patients, particularly those with risk factors for skin cancer.

Cervical Cancer

A population-based retrospective cohort study using data from Swedish national health registries found a 2 to 3 fold increase in the incidence of invasive cervical cancer in women with RA treated with Infliximab compared to biologics-naïve patients or the general population, particularly those over 60 years of age. A causal relationship between Infliximab and cervical cancer cannot be excluded. Periodic screening should continue in women treated with Infliximab [see Adverse Reactions (6.3)] .

Other Malignancies

In the controlled portions of clinical trials of some TNF blockers including Infliximab, more malignancies (excluding lymphoma and nonmelanoma skin cancer [NMSC]) have been observed in patients receiving those TNF blockers compared with control patients. During the controlled portions of Infliximab trials in patients with moderately to severely active RA, CD, PsA, AS, UC, and Ps, 14 patients were diagnosed with malignancies (excluding lymphoma and NMSC) among 4019 Infliximab-treated patients vs. 1 among 1597 control patients (at a rate of 0.52/100 patient-years among Infliximab-treated patients vs. a rate of 0.11/100 patient-years among control patients), with median duration of follow-up 0.5 years for Infliximab-treated patients and 0.4 years for control patients. Of these, the most common malignancies were breast, colorectal, and melanoma. The rate of malignancies among Infliximab-treated patients was similar to that expected in the general population whereas the rate in control patients was lower than expected.

In a clinical trial exploring the use of Infliximab in patients with moderate to severe chronic obstructive pulmonary disease (COPD), more malignancies, the majority of lung or head and neck origin, were reported in Infliximab-treated patients compared with control patients. All patients had a history of heavy smoking [see Adverse Reactions (6.1)] . Prescribers should exercise caution when considering the use of Infliximab in patients with moderate to severe COPD.

Ps patients should be monitored for nonmelanoma skin cancers (NMSCs), particularly those patients who have had prior prolonged phototherapy treatment. In the maintenance portion of clinical trials for Infliximab, NMSCs were more common in patients with previous phototherapy [see Adverse Reactions (6.1)] .

The potential role of TNF blockers in the development of malignancies is not known [see Adverse Reactions (6.1)]. Rates in clinical trials for Infliximab cannot be compared to rates in clinical trials of other TNF blockers and may not predict rates observed in a broader patient population. Caution should be exercised in considering Infliximab treatment in patients with a history of malignancy or in continuing treatment in patients who develop malignancy while receiving Infliximab.

5.3 Hepatitis B Virus Reactivation

Use of TNF blockers, including Infliximab, has been associated with reactivation of hepatitis B virus (HBV) in patients who are chronic carriers of this virus. In some instances, HBV reactivation occurring in conjunction with TNF blocker therapy has been fatal. The majority of these reports have occurred in patients concomitantly receiving other medications that suppress the immune system, which may also contribute to HBV reactivation. Patients should be tested for HBV infection before initiating TNF blocker therapy, including Infliximab. For patients who test positive for hepatitis B surface antigen, consultation with a physician with expertise in the treatment of hepatitis B is recommended. Adequate data are not available on the safety or efficacy of treating patients who are carriers of HBV with anti-viral therapy in conjunction with TNF blocker therapy to prevent HBV reactivation. Patients who are carriers of HBV and require treatment with TNF blockers should be closely monitored for clinical and laboratory signs of active HBV infection throughout therapy and for several months following termination of therapy. In patients who develop HBV reactivation, TNF blockers should be stopped and antiviral therapy with appropriate supportive treatment should be initiated. The safety of resuming TNF blocker therapy after HBV reactivation is controlled is not known. Therefore, prescribers should exercise caution when considering resumption of TNF blocker therapy in this situation and monitor patients closely.

5.4 Hepatotoxicity

Severe hepatic reactions, including acute liver failure, jaundice, hepatitis and cholestasis, have been reported in postmarketing data in patients receiving Infliximab. Autoimmune hepatitis has been diagnosed in some of these cases. Severe hepatic reactions occurred between 2 weeks to more than 1 year after initiation of Infliximab; elevations in hepatic aminotransferase levels were not noted prior to discovery of the liver injury in many of these cases. Some of these cases were fatal or necessitated liver transplantation. Patients with symptoms or signs of liver dysfunction should be evaluated for evidence of liver injury. If jaundice and/or marked liver enzyme elevations (e.g., ≥5 times the upper limit of normal) develop, Infliximab should be discontinued, and a thorough investigation of the abnormality should be undertaken. In clinical trials, mild or moderate elevations of ALT and AST have been observed in patients receiving Infliximab without progression to severe hepatic injury [see Adverse Reactions (6.1)] .

5.5 Heart Failure

The use of Infliximab at doses >5 mg/kg is contraindicated in patients with moderate or severe heart failure. A randomized, double-blind, placebo-controlled study evaluated the use of Infliximab (5 mg/kg or 10 mg/kg at Weeks 0, 2, and 6) in patients with moderate or severe heart failure [New York Heart Association (NYHA) Functional Class III/IV]. Compared to patients who received placebo, there was a higher rate of mortality and a higher risk of hospitalization at Week 28 due to heart failure in patients who received the 10 mg/kg Infliximab dose, and higher rates of cardiovascular adverse events in patients who received Infliximab doses of 5 mg/kg and 10 mg/kg.

There have been post-marketing reports of new onset and worsening heart failure, with and without identifiable precipitating factors (e.g., pre-existing cardiovascular disease), in Infliximab-treated patients. Some of these patients have been under 50 years of age.

If a decision is made to administer Infliximab (≤ 5 mg/kg) to patients with moderate or severe heart failure or to administer Infliximab (any approved dose) to patients with mild heart failure, they should be closely monitored during therapy, and Infliximab should be discontinued if new or worsening symptoms of heart failure appear [see Contraindications (4)and Adverse Reactions (6.1)] .

5.6 Hematologic Reactions

Cases of leukopenia, neutropenia, thrombocytopenia, and pancytopenia, some with a fatal outcome, have been reported in patients receiving Infliximab. The causal relationship to Infliximab therapy remains unclear. Although no high-risk group(s) has been identified, caution should be exercised in patients being treated with Infliximab who have ongoing or a history of significant hematologic abnormalities. All patients should be advised to seek immediate medical attention if they develop signs and symptoms suggestive of blood dyscrasias or infection (e.g., persistent fever) while on Infliximab. Discontinuation of Infliximab therapy should be considered in patients who develop significant hematologic abnormalities.

5.7 Hypersensitivity

Infliximab has been associated with hypersensitivity reactions that vary in their time of onset and required hospitalization in some cases. Most hypersensitivity reactions (including anaphylaxis, urticaria, dyspnea, and/or hypotension), have occurred during or within 2 hours of Infliximab infusion.

However, in some cases, serum sickness-like reactions have been observed in patients after initial Infliximab therapy (i.e., as early as after the second dose), and when Infliximab therapy was reinstituted following an extended period without Infliximab treatment. Symptoms associated with these reactions include fever, rash, headache, sore throat, myalgias, polyarthralgias, hand and facial edema and/or dysphagia. These reactions were associated with a marked increase in antibodies to infliximab, loss of detectable serum concentrations of infliximab, and possible loss of drug efficacy.

Infliximab should be discontinued for severe hypersensitivity reactions. Medications for the treatment of hypersensitivity reactions (e.g., acetaminophen, antihistamines, corticosteroids and/or epinephrine) should be available for immediate use in the event of a reaction [see Dosage and Administration (2.10)and Adverse Reactions (6.1)] .

In RA, CD and Ps clinical trials, re-administration of Infliximab after a period of no treatment resulted in a higher incidence of infusion reactions relative to regular maintenance treatment [see Adverse Reactions (6.1)] . In general, the benefit-risk of re-administration of Infliximab after a period of no-treatment, especially as a re-induction regimen given at weeks 0, 2 and 6, should be carefully considered. In the case where Infliximab maintenance therapy for Ps is interrupted, Infliximab should be reinitiated as a single dose followed by maintenance therapy.

5.8 Cardiovascular and Cerebrovascular Reactions During and After Infusion

Serious cerebrovascular accidents, myocardial ischemia/infarction (some fatal), hypotension, hypertension, and arrhythmias have been reported during and within 24 hours of initiation of Infliximab infusion. Cases of transient visual loss have been reported during or within 2 hours of infusion of Infliximab. Monitor patients during infusion and if serious reaction occurs, discontinue infusion. Further management of reactions should be dictated by signs and symptoms [see Adverse Reactions (6)] .

5.9 Neurologic Reactions

Infliximab and other agents that inhibit TNF have been associated with CNS manifestation of systemic vasculitis, seizure and new onset or exacerbation of clinical symptoms and/or radiographic evidence of central nervous system demyelinating disorders, including multiple sclerosis and optic neuritis, and peripheral demyelinating disorders, including Guillain-Barré syndrome. Prescribers should exercise caution in considering the use of Infliximab in patients with these neurologic disorders and should consider discontinuation of Infliximab if these disorders develop.

5.10 Concurrent Administration with Other Biological Products

Serious infections and neutropenia were seen in clinical studies with concurrent use of anakinra and another TNF blocker, etanercept, with no added clinical benefit compared to etanercept alone. Because of the nature of the adverse reactions seen with the concurrent use of etanercept and anakinra therapy, similar toxicities may also result from the concurrent use of anakinra and other TNF blockers. Therefore, the concurrent use of Infliximab and anakinra is not recommended.

In clinical studies, concurrent administration of TNF blockers and abatacept have been associated with an increased risk of infections including serious infections compared with TNF blockers alone, without increased clinical benefit. Therefore, the concurrent use of Infliximab and abatacept is not recommended [see Drug Interactions (7.1)] .

There is insufficient information regarding the concurrent use of Infliximab with other biological products used to treat the same conditions as Infliximab. The concurrent use of Infliximab with these biological products is not recommended because of the possibility of an increased risk of infection [see Drug Interactions (7.1)] .

5.11 Switching Between Biological Disease-Modifying Antirheumatic Drugs (DMARDs)

Care should be taken when switching from one biologic to another, since overlapping biological activity may further increase the risk of infection.

5.12 Autoimmunity

Treatment with Infliximab may result in the formation of autoantibodies and in the development of a lupus-like syndrome. If a patient develops symptoms suggestive of a lupus-like syndrome following treatment with Infliximab, treatment should be discontinued [see Adverse Reactions (6.1)] .

5.13 Vaccinations and Use of Live Vaccines/Therapeutic Infectious Agents

Vaccinations

Prior to initiating Infliximab in pediatric and adult patients, update vaccinations in accordance with current vaccination guidelines.

Live Vaccines and Therapeutic Infectious Agents

In patients receiving TNF blockers, limited data are available on the response to vaccination with live vaccines or on the secondary transmission of infection by live vaccines. Use of live vaccines can result in clinical infections, including disseminated infections. The concurrent administration of live vaccines with Infliximab is not recommended.

Fatal outcome due to disseminated BCG infection has been reported in an infant who received a BCG vaccine after in uteroexposure to infliximab. Infliximab is known to cross the placenta and has been detected up to 6 months following birth. At least a six month waiting period following birth is recommended before the administration of any live vaccine to infants exposed in uteroto infliximab.

Other uses of therapeutic infectious agents such as live attenuated bacteria (e.g., BCG bladder instillation for the treatment of cancer) could result in clinical infections, including disseminated infections. It is recommended that therapeutic infectious agents not be given concurrently with Infliximab.

6 ADVERSE REACTIONS

6.1 Clinical Trials Experience

Because clinical trials are conducted under widely varying conditions, adverse reaction rates observed in the clinical trials of a drug cannot be directly compared to rates in the clinical trials of another drug and may not reflect the rates observed in practice.

Adverse Reactions in Adults

The data described herein reflect exposure to Infliximab in 4779 adult patients (1304 patients with RA, 1106 patients with CD, 202 with AS, 293 with PsA, 484 with UC, 1373 with Ps, and 17 patients with other conditions), including 2625 patients exposed beyond 30 weeks and 374 exposed beyond 1 year. [For information on adverse reactions in pediatric patients see Adverse Reactions (6.1)] .One of the most-common reasons for discontinuation of treatment was infusion-related reactions (e.g., dyspnea, flushing, headache and rash).

Infusion-Related Reactions

Adverse Reactions During or Shortly After Infusion

An infusion reaction was defined in clinical trials as any adverse event occurring during an infusion or within 1 hour after an infusion. In all the clinical studies, approximately 20% of Infliximab-treated patients experienced an infusion reaction compared with 10% of placebo-treated patients. Of Infliximab-treated patients who had an infusion reaction during the induction period, 27% experienced an infusion reaction during the maintenance period. Of patients who did not have an infusion reaction during the induction period, 9% experienced an infusion reaction during the maintenance period.

Among all Infliximab infusions, 3% were accompanied by nonspecific symptoms such as fever or chills, 1% were accompanied by cardiopulmonary reactions (primarily chest pain, hypotension, hypertension or dyspnea), and <1% were accompanied by pruritus, urticaria, or the combined symptoms of pruritus/urticaria and cardiopulmonary reactions. Serious infusion reactions occurred in <1% of patients and included anaphylaxis, convulsions, erythematous rash and hypotension. Approximately 3% of patients discontinued Infliximab because of infusion reactions, and all patients recovered with treatment and/or discontinuation of the infusion. Infliximab infusions beyond the initial infusion were not associated with a higher incidence of reactions. The infusion reaction rates remained stable in Ps through 1 year in Ps Study I. In psoriasis Study II, the rates were variable over time and somewhat higher following the final infusion than after the initial infusion. Across the 3 Ps studies, the percent of total infusions resulting in infusion reactions (i.e., an adverse event occurring within 1 hour) was 7% in the 3 mg/kg group, 4% in the 5 mg/kg group, and 1% in the placebo group.

Patients who became positive for antibodies to infliximab were more likely (approximately two-to three-fold) to have an infusion reaction than were those who were negative. Use of concomitant immunosuppressant agents appeared to reduce the frequency of both antibodies to infliximab and infusion reactions [see Adverse Reactions (6.2)and Drug Interactions (7.3)] .

Infusion Reactions Following Re-administration

In a clinical trial of patients with moderate to severe Ps designed to assess the efficacy of long-term maintenance therapy versus re-treatment with an induction regimen of Infliximab following disease flare, 4% (8/219) of patients in the re-treatment induction therapy arm experienced serious infusion reactions versus <1% (1/222) in the maintenance therapy arm. Patients enrolled in this trial did not receive any concomitant immunosuppressant therapy. In this study, the majority of serious infusion reactions occurred during the second infusion at Week 2. Symptoms included, but were not limited to, dyspnea, urticaria, facial edema, and hypotension. In all cases, Infliximab treatment was discontinued and/or other treatment instituted with complete resolution of signs and symptoms.

Delayed Reactions/Reactions Following Re-administration

In Ps studies, approximately 1% of Infliximab-treated patients experienced a possible delayed hypersensitivity reaction, generally reported as serum sickness or a combination of arthralgia and/or myalgia with fever and/or rash. These reactions generally occurred within 2 weeks after repeat infusion.

Infections

In Infliximab clinical studies, treated infections were reported in 36% of Infliximab-treated patients (average of 51 weeks of follow-up) and in 25% of placebo-treated patients (average of 37 weeks of follow-up). The infections most frequently reported were respiratory tract infections (including sinusitis, pharyngitis, and bronchitis) and urinary tract infections. Among Infliximab-treated patients, serious infections included pneumonia, cellulitis, abscess, skin ulceration, sepsis, and bacterial infection. In clinical trials, 7 opportunistic infections were reported; 2 cases each of coccidioidomycosis (1 case was fatal) and histoplasmosis (1 case was fatal), and 1 case each of pneumocystosis, nocardiosis and cytomegalovirus. Tuberculosis (TB) was reported in 14 patients, 4 of whom died due to miliary tuberculosis. Other cases of TB, including disseminated TB, also have been reported post-marketing. Most of these cases of TB occurred within the first 2 months after initiation of therapy with Infliximab and may reflect recrudescence of latent disease [see Warnings and Precautions (5.1)] . In the 1-year placebo-controlled studies RA I and RA II, 5.3% of patients receiving Infliximab every 8 weeks with MTX developed serious infections as compared to 3.4% of placebo patients receiving MTX. Of 924 patients receiving Infliximab, 1.7% developed pneumonia and 0.4% developed TB, when compared to 0.3% and 0.0% in the placebo arm respectively. In a shorter (22-week) placebo-controlled study of 1082 RA patients randomized to receive placebo, 3 mg/kg or 10 mg/kg Infliximab infusions at 0, 2, and 6 weeks, followed by every 8 weeks with MTX, serious infections were more frequent in the 10 mg/kg Infliximab group (5.3%) than the 3 mg/kg or placebo groups (1.7% in both). During the 54-week Crohn's II Study, 15% of patients with fistulizing CD developed a new fistula-related abscess.

In Infliximab clinical studies in patients with UC, infections treated with antimicrobials were reported in 27% of Infliximab-treated patients (average of 41 weeks of follow-up) and in 18% of placebo-treated patients (average 32 weeks of follow-up). The types of infections, including serious infections, reported in patients with UC were similar to those reported in other clinical studies.

The onset of serious infections may be preceded by constitutional symptoms such as fever, chills, weight loss, and fatigue. The majority of serious infections, however, may also be preceded by signs or symptoms localized to the site of the infection.

Autoantibodies/Lupus-like Syndrome

Approximately half of Infliximab-treated patients in clinical trials who were antinuclear antibody (ANA) negative at baseline developed a positive ANA during the trial compared with approximately one-fifth of placebo-treated patients. Anti-dsDNA antibodies were newly detected in approximately one-fifth of Infliximab-treated patients compared with 0% of placebo-treated patients. Reports of lupus and lupus-like syndromes, however, remain uncommon.

Malignancies

In controlled trials, more Infliximab-treated patients developed malignancies than placebo-treated patients [see Warnings and Precautions (5.2)] .

In a randomized controlled clinical trial exploring the use of Infliximab in patients with moderate to severe COPD who were either current smokers or ex-smokers, 157 patients were treated with Infliximab at doses similar to those used in RA and CD. Of these Infliximab-treated patients, 9 developed a malignancy, including 1 lymphoma, for a rate of 7.67 cases per 100 patient-years of follow-up (median duration of follow-up 0.8 years; 95% CI 3.51 – 14.56). There was 1 reported malignancy among 77 control patients for a rate of 1.63 cases per 100 patient-years of follow-up (median duration of follow-up 0.8 years; 95% CI 0.04 – 9.10). The majority of the malignancies developed in the lung or head and neck [see Warnings and Precautions (5.2)] .

Adverse Reactions in Patients with NYHA Class III/IV Heart Failure

In a randomized, double-blind study evaluating Infliximab in moderate or severe heart failure (NYHA Class III/IV; left ventricular ejection fraction ≤35%), 150 patients were randomized to receive treatment with 3 infusions of Infliximab 10 mg/kg, 5 mg/kg, or placebo, at 0, 2, and 6 weeks. Higher incidences of mortality and hospitalization due to worsening heart failure were observed in patients receiving the 10 mg/kg Infliximab dose. At 1 year, 8 patients in the 10 mg/kg Infliximab group had died compared with 4 deaths each in the 5 mg/kg Infliximab and the placebo groups. There were trends toward increased dyspnea, hypotension, angina, and dizziness in both the 10 mg/kg and 5 mg/kg Infliximab treatment groups, versus placebo. Infliximab has not been studied in patients with mild heart failure (NYHA Class I/II) [see Contraindications (4)and Warnings and Precautions (5.5)] .

Hepatotoxicity

Severe liver injury, including acute liver failure and autoimmune hepatitis, has been reported in patients receiving Infliximab [see Warnings and Precautions (5.4)] . Reactivation of hepatitis B virus has occurred in patients receiving TNF blockers, including Infliximab, who are chronic carriers of this virus [see Warnings and Precautions (5.3)] .

In clinical trials in RA, CD, UC, AS, Ps, and PsA, elevations of aminotransferases were observed (ALT more common than AST) in a greater proportion of patients receiving Infliximab than in controls (Table 1), both when Infliximab was given as monotherapy and when it was used in combination with other immunosuppressive agents. In general, patients who developed ALT and AST elevations were asymptomatic, and the abnormalities decreased or resolved with either continuation or discontinuation of Infliximab, or modification of concomitant medications.

Table 1: Proportion of Patients with Elevated ALT in Clinical Trials in Adults
 | Proportion of patients with elevated ALT
 | >1 to <3 × ULN |  | ≥3 × ULN |  | ≥5 × ULN
 | Placebo | Infliximab | Placebo | Infliximab | Placebo | Infliximab
Rheumatoid arthritis [Placebo patients received methotrexate while Infliximab patients received both Infliximab and methotrexate. Median follow-up was 58 weeks.] | 24% | 34% | 3% | 4% | <1% | <1%
Crohn's disease [Placebo patients in the 2 Phase 3 trials in CD received an initial dose of 5 mg/kg Infliximab at study start and were on placebo in the maintenance phase. Patients who were randomized to the placebo maintenance group and then later crossed over to Infliximab are included in the Infliximab group in ALT analysis. Median follow-up was 54 weeks.] | 34% | 39% | 4% | 5% | 0% | 2%
Ulcerative colitis [Median follow-up was 30 weeks. Specifically, the median duration of follow-up was 30 weeks for placebo and 31 weeks for Infliximab.] | 12% | 17% | 1% | 2% | <1% | <1%
Ankylosing spondylitis [Median follow-up was 24 weeks for the placebo group and 102 weeks for the Infliximab group.] | 15% | 51% | 0% | 10% | 0% | 4%
Psoriatic arthritis [Median follow-up was 39 weeks for the Infliximab group and 18 weeks for the placebo group.] | 16% | 50% | 0% | 7% | 0% | 2%
Plaque psoriasis [ALT values are obtained in 2 Phase 3 Ps studies with median follow-up of 50 weeks for Infliximab and 16 weeks for placebo.] | 24% | 49% | <1% | 8% | 0% | 3%

Adverse Reactions in Psoriasis Studies

During the placebo-controlled portion across the 3 clinical trials up to Week 16, the proportion of patients who experienced at least 1 serious adverse reaction (SAE; defined as resulting in death, life threatening, requires hospitalization, or persistent or significant disability/incapacity) was 0.5% in the 3 mg/kg Infliximab group, 1.9% in the placebo group, and 1.6% in the 5 mg/kg Infliximab group.

Among patients in the 2 Phase 3 studies, 12.4% of patients receiving Infliximab 5 mg/kg every 8 weeks through 1 year of maintenance treatment experienced at least 1 SAE in Study I. In Study II, 4.1% and 4.7% of patients receiving Infliximab 3 mg/kg and 5 mg/kg every 8 weeks, respectively, through 1 year of maintenance treatment experienced at least 1 SAE.

One death due to bacterial sepsis occurred 25 days after the second infusion of 5 mg/kg Infliximab. Serious infections included sepsis, and abscesses. In Study I, 2.7% of patients receiving Infliximab 5 mg/kg every 8 weeks through 1 year of maintenance treatment experienced at least 1 serious infection. In Study II, 1.0% and 1.3% of patients receiving Infliximab 3 mg/kg and 5 mg/kg, respectively, through 1 year of treatment experienced at least 1 serious infection. The most common serious infection (requiring hospitalization) was abscess (skin, throat, and peri-rectal) reported by 5 (0.7%) patients in the 5 mg/kg Infliximab group. Two active cases of tuberculosis were reported: 6 weeks and 34 weeks after starting Infliximab.

In the placebo-controlled portion of the Ps studies, 7 of 1123 patients who received Infliximab at any dose were diagnosed with at least one NMSC compared to 0 of 334 patients who received placebo.

In the Ps studies, 1% (15/1373) of patients experienced serum sickness or a combination of arthralgia and/or myalgia with fever, and/or rash, usually early in the treatment course. Of these patients, 6 required hospitalization due to fever, severe myalgia, arthralgia, swollen joints, and immobility.

Other Adverse Reactions in Adults

Safety data are available from 4779 Infliximab-treated adult patients, including 1304 with RA, 1106 with CD, 484 with UC, 202 with AS, 293 with PsA, 1373 with Ps and 17 with other conditions. [For information on other adverse reactions in pediatric patients, see Adverse Reactions (6.1)]. Adverse reactions reported in ≥5% of all patients with RA receiving 4 or more infusions are in Table 2. The types and frequencies of adverse reactions observed were similar in Infliximab-treated RA, AS, PsA, Ps, and CD patients except for abdominal pain, which occurred in 26% of Infliximab-treated patients with CD. In the CD studies, there were insufficient numbers and duration of follow-up for patients who never received Infliximab to provide meaningful comparisons.

Table 2: Adverse Reactions that Occurred in ≥ 5% of Patients who Received ≥ 4 Infliximab Infusions for RA
 | Placebo | Infliximab
 | (n=350) | (n=1129)
Average weeks of follow-up | 59 weeks | 66 weeks
Upper respiratory tract infection | 25% | 32%
Nausea | 20% | 21%
Headache | 14% | 18%
Sinusitis | 8% | 14%
Diarrhea | 12% | 12%
Abdominal pain | 8% | 12%
Pharyngitis | 8% | 12%
Coughing | 8% | 12%
Bronchitis | 9% | 10%
Rash | 5% | 10%
Dyspepsia | 7% | 10%
Fatigue | 7% | 9%
Urinary tract infection | 6% | 8%
Pain | 7% | 8%
Arthralgia | 7% | 8%
Pruritus | 2% | 7%
Fever | 4% | 7%
Hypertension | 5% | 7%
Moniliasis | 3% | 5%

The most common serious adverse reactions observed in clinical trials were infections [see Adverse Reactions (6.1)] . Other serious, medically relevant adverse reactions ≥0.2% or clinically significant adverse reactions by body system were as follows:

- Body as a whole: allergic reaction, edema
- Blood: pancytopenia
- Cardiovascular: hypotension
- Gastrointestinal: constipation, intestinal obstruction
- Central and Peripheral Nervous: dizziness
- Heart Rate and Rhythm: bradycardia
- Liver and Biliary: hepatitis
- Metabolic and Nutritional: dehydration
- Platelet, Bleeding and Clotting: thrombocytopenia
- Neoplasms: lymphoma
- Red Blood Cell: anemia, hemolytic anemia
- Resistance Mechanism: cellulitis, sepsis, serum sickness, sarcoidosis
- Respiratory: lower respiratory tract infection (including pneumonia), pleurisy, pulmonary edema
- Skin and Appendages: increased sweating
- Vascular (Extracardiac): thrombophlebitis
- White Cell and Reticuloendothelial: leukopenia, lymphadenopathy

Adverse Reactions in Pediatric Patients

Adverse Reactions in Pediatric Patients with Crohn's Disease

There were some differences in the adverse reactions observed in the pediatric patients receiving Infliximab compared to those observed in adults with CD. These differences are discussed in the following paragraphs.

The following adverse reactions were reported more commonly in 103 randomized pediatric CD patients administered 5 mg/kg Infliximab through 54 weeks than in 385 adult CD patients receiving a similar treatment regimen: anemia (11%), leukopenia (9%), flushing (9%), viral infection (8%), neutropenia (7%), bone fracture (7%), bacterial infection (6%), and respiratory tract allergic reaction (6%).

Infections were reported in 56% of randomized pediatric patients in Study Peds Crohn's and in 50% of adult patients in Study Crohn's I. In Study Peds Crohn's, infections were reported more frequently for patients who received every 8-week as opposed to every 12-week infusions (74% and 38%, respectively), while serious infections were reported for 3 patients in the every 8-week and 4 patients in the every 12-week maintenance treatment group. The most commonly reported infections were upper respiratory tract infection and pharyngitis, and the most commonly reported serious infection was abscess. Pneumonia was reported for 3 patients, (2 in the every 8-week and 1 in the every 12-week maintenance treatment groups). Herpes zoster was reported for 2 patients in the every 8-week maintenance treatment group.

In Study Peds Crohn's, 18% of randomized patients experienced 1 or more infusion reactions, with no notable difference between treatment groups. Of the 112 patients in Study Peds Crohn's, there were no serious infusion reactions, and 2 patients had non-serious anaphylactoid reactions.

Elevations of ALT up to 3 times the upper limit of normal (ULN) were seen in 18% of pediatric patients in CD clinical trials; 4% had ALT elevations ≥3 × ULN, and 1% had elevations ≥5 × ULN. (Median follow-up was 53 weeks).

Adverse Reactions in Pediatric Patients with Ulcerative Colitis

Overall, the adverse reactions reported in the pediatric UC trial and adult UC (Study UC I and Study UC II) studies were generally consistent. In a pediatric UC trial, the most common adverse reactions were upper respiratory tract infection, pharyngitis, abdominal pain, fever, and headache.

Infections were reported in 31 (52%) of 60 treated patients in the pediatric UC trial and 22 (37%) required oral or parenteral antimicrobial treatment. The proportion of patients with infections in the pediatric UC trial was similar to that in the pediatric CD study (Study Peds Crohn's) but higher than the proportion in the adults' UC studies (Study UC I and Study UC II). The overall incidence of infections in the pediatric UC trial was 13/22 (59%) in the every 8 week maintenance treatment group. Upper respiratory tract infection (7/60 [12%]) and pharyngitis (5/60 [8%]) were the most frequently reported respiratory system infections. Serious infections were reported in 12% (7/60) of all treated patients.

Elevations of ALT up to 3 times the upper limit of normal (ULN) were seen in 17% (10/60) of pediatric patients in the pediatric UC trial; 7% (4/60) had ALT elevations ≥3 × ULN, and 2% (1/60) had elevations ≥5 × ULN (median follow-up was 49 weeks).

Overall, 8 of 60 (13%) treated patients experienced one or more infusion reactions, including 4 of 22 (18%) patients in the every 8-week treatment maintenance group. No serious infusion reactions were reported.

In the pediatric UC trial, 45 patients were in the 12 to 17 year age group and 15 in the 6 to 11 year age group. The numbers of patients in each subgroup are too small to make any definitive conclusions about the effect of age on safety events. There were higher proportions of patients with serious adverse events (40% vs. 18%) and discontinuation due to adverse events (40% vs. 16%) in the younger age group than in the older age group. While the proportion of patients with infections was also higher in the younger age group (60% vs. 49%), for serious infections, the proportions were similar in the two age groups (13% in the 6 to 11 year age group vs. 11% in the 12 to 17 year age group). Overall proportions of adverse reactions, including infusion reactions, were similar between the 6 to 11 and 12 to 17 year age groups (13%).

6.2 Immunogenicity

As with all therapeutic proteins, there is potential for immunogenicity. The detection of antibody formation is highly dependent on the sensitivity and specificity of the assay. Additionally, the observed incidence of antibody (including neutralizing antibody) positivity in an assay may be influenced by several factors, including assay methodology, sample handling, timing of sample collection, concomitant medications, and underlying disease. For these reasons, comparison of the incidence of antibodies in the studies described below with the incidence of antibodies in other studies or to other infliximab products may be misleading.

Treatment with Infliximab can be associated with the development of antibodies to infliximab. An enzyme immunoassay (EIA) method was originally used to measure anti-infliximab antibodies in clinical studies of Infliximab. The EIA method is subject to interference by serum infliximab, possibly resulting in an underestimation of the rate of patient antibody formation. A separate, drug-tolerant electrochemiluminescence immunoassay (ECLIA) method for detecting antibodies to infliximab was subsequently developed and validated. This method is 60-fold more sensitive than the original EIA. With the ECLIA method, all clinical samples can be classified as either positive or negative for antibodies to infliximab without the need for the inconclusive category.

The incidence of antibodies to infliximab was based on the original EIA method in all clinical studies of Infliximab except for the Phase 3 study in pediatric patients with UC where the incidence of antibodies to infliximab was detected using both the EIA and ECLIA methods.

Immunogenicity in Adult Patients

The incidence of antibodies to infliximab in patients with RA and CD given a 3-dose induction regimen followed by maintenance dosing was approximately 10% as assessed through 1 to 2 years of Infliximab treatment. A higher incidence of antibodies to infliximab was observed in CD patients receiving Infliximab after drug-free intervals >16 weeks. In a PsA study in which 191 patients received 5 mg/kg with or without MTX, antibodies to infliximab occurred in 15% of patients. The majority of antibody-positive patients had low titers. Antibody development was lower among RA and CD patients receiving immunosuppressant therapies such as 6-MP/AZA or MTX. Patients who were antibody-positive were more likely to have higher rates of clearance, have reduced efficacy, and to experience an infusion reaction than were patients who were antibody negative [see Adverse Reactions (6.1)] . In the Ps Study II, which included both the 5 mg/kg and 3 mg/kg doses, antibodies were observed in 36% of patients treated with 5 mg/kg every 8 weeks for 1 year, and in 51% of patients treated with 3 mg/kg every 8 weeks for 1 year.

In the Ps Study III, which also included both the 5 mg/kg and 3 mg/kg doses, antibodies were observed in 20% of patients treated with 5 mg/kg induction (weeks 0, 2 and 6), and in 27% of patients treated with 3 mg/kg induction. Despite the increase in antibody formation, the infusion reaction rates in Studies I and II in patients treated with 5 mg/kg induction followed by every 8 week maintenance for 1 year and in Study III in patients treated with 5 mg/kg induction (14.1%–23.0%) and serious infusion reaction rates (<1%) were similar to those observed in other study populations. The clinical significance of apparent increased immunogenicity on efficacy and infusion reactions in Ps patients as compared to patients with other diseases treated with Infliximab over the long term is not known.

Immunogenicity in Pediatric Patients with Crohn's Disease

In Study Peds Crohn's, in which all patients received stable doses of 6-MP, AZA, or MTX, excluding inconclusive samples, 3 of 24 patients had antibodies to infliximab. Although 105 patients were tested for antibodies to infliximab, 81 patients were classified as inconclusive because they could not be ruled as negative due to assay interference by the presence of infliximab in the sample.

Immunogenicity in Pediatric Patients with Ulcerative Colitis

In the pediatric UC trial, 58 patients were evaluated for antibodies to infliximab using the EIA as well as the drug-tolerant ECLIA. With the EIA, 4 of 58 (7%) patients had antibodies to infliximab. With the ECLIA, 30 of 58 (52%) patients had antibodies to infliximab. The higher incidence of antibodies to infliximab by the ECLIA method was due to the 60-fold higher sensitivity compared to the EIA method. While EIA-positive patients generally had undetectable trough infliximab concentrations, ECLIA-positive patients could have detectable trough concentrations of infliximab because the ECLIA assay is more sensitive and drug-tolerant.

6.3 Postmarketing Experience

Adverse reactions, some with fatal outcomes, have been identified during post approval use of Infliximab in adult and pediatric patients. Because these reactions are reported voluntarily from a population of uncertain size, it is not always possible to reliably estimate their frequency or establish a causal relationship to drug exposure.

Postmarketing Adverse Reactions in Adults and Pediatric Patients

- Neutropenia [see Warnings and Precautions (5.6)] , agranulocytosis (including infants exposed in uteroto infliximab), idiopathic thrombocytopenic purpura, thrombotic thrombocytopenic purpura.
- Interstitial lung disease (including pulmonary fibrosis/interstitial pneumonitis and rapidly progressive disease).
- Pericardial effusion, systemic and cutaneous vasculitis.
- Erythema multiforme, Stevens-Johnson Syndrome, toxic epidermal necrolysis, linear IgA bullous dermatosis (LABD), acute generalized exanthematous pustulosis (AGEP), worsening psoriasis (all subtypes including pustular, primarily palmoplantar), lichenoid reactions.
- Peripheral demyelinating disorders (such as Guillain-Barré syndrome, chronic inflammatory demyelinating polyneuropathy, and multifocal motor neuropathy) transverse myelitis, and neuropathies (additional neurologic reactions have also been observed) [see Warnings and Precautions (5.9)] .
- Acute liver failure, jaundice, hepatitis, and cholestasis [see Warnings and Precautions (5.4)] .
- Serious infections [see Warnings and Precautions (5.1)] and vaccine breakthrough infection including bovine tuberculosis (disseminated BCG infection) following vaccination in an infant exposed in uteroto infliximab [see Warnings and Precautions (5.13)].
- Malignancies, including leukemia, melanoma, Merkel cell carcinoma, and cervical cancer [see Warnings and Precautions (5.2)] .
- Anaphylactic reactions, including anaphylactic shock, laryngeal/pharyngeal edema and severe bronchospasm, and seizure have been associated with Infliximab administration.
- Transient visual loss have been reported in association with Infliximab during or within 2 hours of infusion. Cerebrovascular accidents, myocardial ischemia/infarction (some fatal), and arrhythmia occurring within 24 hours of initiation of infusion have also been reported [see Warnings and Precautions (5.8)] .
- New onset immune disorders (e.g., psoriasis, rheumatoid arthritis, inflammatory bowel disease).

Postmarketing Serious Adverse Reactions in Pediatric Patients

The following serious adverse reactions have been reported in the post-marketing experience in pediatric patients: infections (some fatal) including opportunistic infections and tuberculosis, infusion reactions, hypersensitivity reactions, malignancies, including hepatosplenic T-cell lymphomas [see Boxed Warningand Warnings and Precautions (5.2)] , transient hepatic enzyme abnormalities, lupus-like syndromes, and the development of autoantibodies.

7 DRUG INTERACTIONS

7.1 Other Biological Products

The combination of Infliximab with other biological products used to treat the same conditions as Infliximab is not recommended [see Warnings and Precautions (5.10)] .

An increased risk of serious infections was seen in clinical studies of other TNF blockers used in combination with anakinra or abatacept, with no added clinical benefit. Because of the nature of the adverse reactions seen with these combinations with TNF blocker therapy, similar toxicities may also result from the combination of anakinra or abatacept with other TNF blockers. Therefore, the combination of Infliximab and anakinra or abatacept is not recommended [see Warnings and Precautions (5.10)] .

The concomitant use of tocilizumab with biological DMARDs such as TNF antagonists, including Infliximab, should be avoided because of the possibility of increased immunosuppression and increased risk of infection.

7.2 Methotrexate and Other Concomitant Medications

Specific drug interaction studies, including interactions with methotrexate (MTX), have not been conducted. The majority of patients in RA or CD clinical studies received one or more concomitant medications. In RA, concomitant medications besides MTX were nonsteroidal anti-inflammatory agents (NSAIDs), folic acid, corticosteroids and/or narcotics. Concomitant CD medications were antibiotics, antivirals, corticosteroids, 6-MP/AZA and aminosalicylates. In PsA clinical trials, concomitant medications included MTX in approximately half of the patients as well as NSAIDs, folic acid and corticosteroids. Concomitant MTX use may decrease the incidence of anti-infliximab antibody production and increase infliximab concentrations.

7.3 Immunosuppressants

Patients with CD who received immunosuppressants tended to experience fewer infusion reactions compared to patients on no immunosuppressants [see Adverse Reactions (6.1)] . Serum infliximab concentrations appeared to be unaffected by baseline use of medications for the treatment of CD including corticosteroids, antibiotics (metronidazole or ciprofloxacin) and aminosalicylates.

7.4 Cytochrome P450 Substrates

The formation of CYP450 enzymes may be suppressed by increased levels of cytokines (e.g., TNFα, IL-1, IL-6, IL-10, IFN) during chronic inflammation. Therefore, it is expected that for a molecule that antagonizes cytokine activity, such as infliximab, the formation of CYP450 enzymes could be normalized. Upon initiation or discontinuation of Infliximab in patients being treated with CYP450 substrates with a narrow therapeutic index, monitoring of the effect (e.g., warfarin) or drug concentration (e.g., cyclosporine or theophylline) is recommended and the individual dose of the drug product may be adjusted as needed.

7.5 Live Vaccines/Therapeutic Infectious Agents

It is recommended that live vaccines not be given concurrently with Infliximab. It is also recommended that live vaccines not be given to infants after in uteroexposure to infliximab for at least 6 months following birth [see Warnings and Precautions (5.13)] .

It is recommended that therapeutic infectious agents not be given concurrently with Infliximab [see Warnings and Precautions (5.13)] .

8 USE IN SPECIFIC POPULATIONS

8.1 Pregnancy

Risk Summary

Available observational studies in pregnant women exposed to Infliximab showed no increased risk of major malformations among live births as compared to those exposed to non-biologics. However, findings on other birth and maternal outcomes were not consistent across studies of different study design and conduct (see Data) .

Monoclonal antibodies such as infliximab are transferred across the placenta during the third trimester of pregnancy and may affect immune response in the in uteroexposed infant (see Clinical Considerations) . Because infliximab does not cross-react with TNFα in species other than humans and chimpanzees, animal reproduction studies have not been conducted with Infliximab. In a developmental study conducted in mice using an analogous antibody, no evidence of maternal toxicity or fetal harm was observed (see Data) .

All pregnancies have a background risk of birth defect, loss, or other adverse outcomes.

The estimated background risk of major birth defects and miscarriage for the indicated populations is unknown. In the U.S. general population, the estimated background risks of major birth defects and miscarriage in clinically recognized pregnancies is 2–4% and 15–20%, respectively.

Clinical Considerations

Disease-Associated Maternal and/or Embryo/Fetal Risk

Published data suggest that there is an increased risk of adverse pregnancy outcomes in women with inflammatory bowel disease or rheumatoid arthritis associated with increased disease activity. Adverse pregnancy outcomes include preterm delivery (before 37 weeks of gestation), low birth weight (less than 2.5 kg) and small for gestational age at birth.

Fetal/Neonatal Adverse Reactions

As with other IgG antibodies, infliximab crosses the placenta. Infliximab has been detected in the serum of infants up to 6 months following birth. Consequently, these infants may be at increased risk of infection, including disseminated infection which can become fatal. At least a six month waiting period following birth is recommended before the administration of live vaccines (e.g., BCG vaccine or other live vaccines, such as the rotavirus vaccine) to these infants [see Warnings and Precautions (5.13)] . Cases of agranulocytosis in infants exposed in uterohave also been reported [see Adverse Reactions (6.3)] .

Data

Human Data

Two prospective cohort studies were conducted assessing birth outcomes as well as the health status of infants up to the age of one year in women exposed to Infliximab compared to non-biologic comparators including methotrexate, azathioprine, 6-mercaptopurine and systemic corticosteroids used for the treatment of similar diseases. The first study was conducted in an IBD pregnancy registry in the United States and assessed pregnancy outcomes in 294 women with inflammatory bowel disease exposed to Infliximab during pregnancy compared with 515 women on a non-biologic treatment. Infliximab exposure was not associated with increased rates of major congenital malformations, miscarriage/stillbirth, infants of low birth weight, small for gestational age, or infection in the first year of life. The second study among IBD and non-IBD patients in Sweden, Finland, and Denmark compared 97, 7, and 166 women exposed to Infliximab to 2,693, 2,499 and 1,268 women on non-biologic systemic therapy, respectively. In this study, comparing pooled data across the three countries, exposure to Infliximab was not associated with increased rates of congenital anomalies or infant death. Infliximab in combination with immunosuppressants (mainly systemic corticosteroids and azathioprine) was associated with increased rates of preterm birth, small for gestational age, low birth weight, and infant hospitalization for infection compared with non-biologic systemic treatment. Although the study did not show any associations with Infliximab monotherapy, the analyses could have been underpowered to detect an association.

There were additional methodological limitations with these studies that may account for the study findings in both studies: the concomitant use of other medications or treatments was not controlled and disease severity was not assessed; in the U.S. study, patient reported outcomes were collected without clinical validation. These methodological limitations hinder interpretation of the study results.

Animal Data

Because infliximab products do not cross-react with TNFα in species other than humans and chimpanzees, animal reproduction studies have not been conducted with infliximab. An embryofetal development study was conducted in pregnant mice using cV1q anti-mouse TNFα, an analogous antibody that selectively inhibits the functional activity of mouse TNFα. This antibody administered in mice, during the period of organogenesis on gestation days (GDs) 6 and 12, at IV doses up to 40 mg/kg produced no evidence of maternal toxicity, fetal mortality, or structural abnormalities. Doses of 10 to 15 mg/kg in pharmacodynamic animal models with the anti-TNF analogous antibody produced maximal pharmacologic effectiveness. Analyses of fetal samples on GD 14 indicated placental transfer of the antibody and exposure of the fetuses during organogenesis. In a peri- and post-natal development study in mice, no maternal toxicity or adverse developmental effects in offspring were observed when dams were administered IV doses of 10 or 40 mg/kg of the analogous antibody on GDs 6, 12 and 18 and lactation days 3, 9 and 15.

8.2 Lactation

Risk Summary

Published literature show that infliximab is present at low levels in human milk. Systemic exposure in a breastfed infant is expected to be low because infliximab is largely degraded in the gastrointestinal tract. A U.S. multi-center study of 168 women treated with infliximab for inflammatory bowel disease (breast milk samples obtained, n=29) showed that infants exposed to infliximab through breast milk had no increase in rates of infections and developed normally. There are no data on the effects of infliximab on milk production. The developmental and health benefits of breastfeeding should be considered along with the mother's clinical need for Infliximab and any potential adverse effects on the breastfed child from Infliximab or from the underlying maternal condition.

8.4 Pediatric Use

The safety and effectiveness of Infliximab have been established in pediatric patients 6 to 17 years of age for induction and maintenance treatment of CD and UC [see Dosage and Administration (2.2, 2.4)and Adverse Reactions (6.1)] . However, the safety and effectiveness of Infliximab in pediatric patients <6 years of age with CD or UC have not been established. The safety and effectiveness of Infliximab in the treatment of pediatric patients with Ps and juvenile rheumatoid arthritis (JRA) have not been established.

Pediatric Crohn's Disease

The safety and effectiveness of Infliximab have been established for reducing signs and symptoms and inducing and maintaining clinical remission in pediatric patients 6 years of age and older with moderately to severely active CD who have had an inadequate response to conventional therapy. The use of Infliximab for this indication is supported by evidence from a randomized, open-label pediatric CD study in 112 pediatric patients aged 6 years and older [see Clinical Studies (14.2)].

Infliximab has been studied only in combination with conventional immunosuppressive therapy in pediatric CD. The longer term (greater than 1 year) safety and effectiveness of Infliximab in pediatric CD patients have not been established in clinical trials.

Postmarketing cases of HSTCL have been reported in pediatric patients treated with TNF blockers including Infliximab. Due to the risk of HSTCL, a careful risk-benefit assessment should be made when Infliximab is used in combination with other immunosuppressants in pediatric CD patients [see Boxed Warningand Warnings and Precautions (5.2)].

Pediatric Ulcerative Colitis

The safety and effectiveness of Infliximab for reducing signs and symptoms and inducing and maintaining clinical remission in pediatric patients aged 6 years and older with moderately to severely active UC who have had an inadequate response to conventional therapy have been established. The use of Infliximab for this indication is supported by evidence from adequate and well-controlled studies of Infliximab in adults with additional safety and pharmacokinetic data from an open-label pediatric UC study in 60 pediatric patients aged 6 years and older [see Dosage and Administration (2.4), Adverse Reactions (6.1), and Clinical Studies (14.4)] . The effectiveness of Infliximab in inducing and maintaining mucosal healing in pediatric UC was not established. Although 41 patients had a Mayo endoscopy subscore of 0 or 1 at the Week 8 endoscopy, the induction phase was open-label and lacked a control group. Only 9 patients had an optional endoscopy at Week 54. Approximately half of the patients were on concomitant immunomodulators (AZA, 6-MP, MTX) at study start.

Due to the risk of HSTCL, a careful risk-benefit assessment should be made when Infliximab is used in combination with other immunosuppressants in pediatric UC patients [see Boxed Warningand Warnings and Precautions (5.2)] .

The longer term (greater than 1 year) safety and effectiveness of Infliximab in pediatric UC patients have not been established in clinical trials.

Juvenile Rheumatoid Arthritis (JRA)

The safety and effectiveness of Infliximab in the treatment of pediatric patients with juvenile rheumatoid arthritis (JRA) have notbeen established.

The safety and efficacy of Infliximab in patients with JRA were evaluated in a multicenter, randomized, placebo-controlled, double-blind study for 14 weeks, followed by a double-blind, all-active treatment extension, for a maximum of 44 weeks. Patients with active JRA between the ages of 4 and 17 years who had been treated with MTX for at least 3 months were enrolled. Concurrent use of folic acid, oral corticosteroids (≤0.2 mg/kg/day of prednisone or equivalent), NSAIDs, and/or disease modifying antirheumatic drugs (DMARDs) was permitted.

Doses of 3 mg/kg Infliximab or placebo were administered intravenously at Weeks 0, 2 and 6. Patients randomized to placebo crossed-over to receive 6 mg/kg Infliximab at Weeks 14, 16, and 20, and then every 8 weeks through Week 44. Patients who completed the study continued to receive open-label treatment with Infliximab for up to 2 years in a companion extension study.

The study failed to establish the efficacy of Infliximab in the treatment of JRA. Key observations in the study included a high placebo response rate and a higher rate of immunogenicity than what has been observed in adults. Additionally, a higher rate of clearance of infliximab was observed than had been observed in adults.

Population pharmacokinetic analysis showed that in pediatric patients with JRA with a body weight of up to 35 kg receiving 6 mg/kg Infliximab and pediatric patients with JRA with body weight greater than 35 kg up to adult body weight receiving 3 mg/kg Infliximab, the steady state area under the concentration curve (AUCss) was similar to that observed in adults receiving 3 mg/kg of Infliximab.

A total of 60 patients with JRA were treated with doses of 3 mg/kg and 57 patients were treated with doses of 6 mg/kg. The proportion of patients with infusion reactions who received 3 mg/kg Infliximab was 35% (21/60) over 52 weeks compared with 18% (10/57) in patients who received 6 mg/kg over 38 weeks. The most common infusion reactions reported were vomiting, fever, headache, and hypotension. In the 3 mg/kg Infliximab group, 4 patients had a serious infusion reaction and 3 patients reported a possible anaphylactic reaction (2 of which were among the serious infusion reactions). In the 6 mg/kg Infliximab group, 2 patients had a serious infusion reaction, 1 of whom had a possible anaphylactic reaction. Two of the 6 patients who experienced serious infusion reactions received Infliximab by rapid infusion (duration of less than 2 hours). Antibodies to infliximab developed in 38% (20/53) of patients who received 3 mg/kg Infliximab compared with 12% (6/49) of patients who received 6 mg/kg.

A total of 68% (41/60) of patients who received 3 mg/kg Infliximab in combination with MTX experienced an infection over 52 weeks compared with 65% (37/57) of patients who received 6 mg/kg Infliximab in combination with MTX over 38 weeks. The most commonly reported infections were upper respiratory tract infection and pharyngitis, and the most commonly reported serious infection was pneumonia. Other notable infections included primary varicella infection in 1 patient and herpes zoster in 1 patient.

8.5 Geriatric Use

Of the total number of Infliximab-treated patients in RA and Ps clinical studies, 256 (9.6%) were 65 years old and over, while 17 (0.6%) were 75 years old and over. In these trials, no overall differences in safety or effectiveness were observed between geriatric patients (patients ≥ 65 years old) and younger adult patients (patients 18 to 65 years old). However, the incidence of serious adverse reactions in geriatric patients was higher in both Infliximab and control groups compared to younger adult patients.

Of the total number of Infliximab-treated patients in CD, UC, AS, and PsA clinical studies, 76 (3.2%) were 65 years old and over, while 9 (0.4%) were 75 years old and over. In the CD, UC, AS, and PsA studies, there were insufficient numbers of geriatric patients to determine whether they respond differently from younger adults .

The incidence of serious infections in Infliximab-treated geriatric patients was greater than in Infliximab-treated younger adult patients; therefore close monitoring of geriatric patients for the development of serious infections is recommended [see Warnings and Precautions (5.1)and Adverse Reactions (6.1)] .

10 OVERDOSAGE

Single doses up to 20 mg/kg have been administered without any direct toxic effect. In case of overdosage, it is recommended that the patient be monitored for any signs or symptoms of adverse reactions or effects [see Warnings and Precautions (5)] and appropriate symptomatic treatment instituted immediately.

11 DESCRIPTION

Infliximab, a tumor necrosis factor (TNF) blocker, is a chimeric IgG1κ monoclonal antibody (composed of human constant and murine variable regions). It has a molecular weight of approximately 149.1 kilodaltons. Infliximab is produced by a recombinant murine myeloma cell line, SP2/0.

Infliximab for injection is supplied as a sterile, preservative-free, white, lyophilized powder for intravenous infusion after reconstitution and dilution. Following reconstitution with 10 mL of Sterile Water for Injection, USP, the final concentration is 10 mg/mL and the resulting pH is approximately 7.2. Each single-dose vial contains 100 mg infliximab, dibasic sodium phosphate, dihydrate (6.1 mg), monobasic sodium phosphate, monohydrate (2.2 mg), polysorbate 80 (0.5 mg), and sucrose (500 mg).

12 CLINICAL PHARMACOLOGY

12.1 Mechanism of Action

Infliximab neutralizes the biological activity of TNFα by binding with high affinity to the soluble and transmembrane forms of TNFα and inhibits binding of TNFα with its receptors. Infliximab does not neutralize TNFβ (lymphotoxin-α), a related cytokine that utilizes the same receptors as TNFα. Biological activities attributed to TNFα include: induction of pro-inflammatory cytokines such as interleukins (IL) 1 and 6, enhancement of leukocyte migration by increasing endothelial layer permeability and expression of adhesion molecules by endothelial cells and leukocytes, activation of neutrophil and eosinophil functional activity, induction of acute phase reactants and other liver proteins, as well as tissue degrading enzymes produced by synoviocytes and/or chondrocytes. Cells expressing transmembrane TNFα bound by infliximab can be lysed in vitroor in vivo. Infliximab inhibits the functional activity of TNFα in a wide variety of in vitrobioassays utilizing human fibroblasts, endothelial cells, neutrophils, B and T-lymphocytes and epithelial cells. The relationship of these biological response markers to the mechanism(s) by which Infliximab exerts its clinical effects is unknown. Anti-TNFα antibodies reduce disease activity in the cotton-top tamarin colitis model, and decrease synovitis and joint erosions in a murine model of collagen-induced arthritis. Infliximab prevents disease in transgenic mice that develop polyarthritis as a result of constitutive expression of human TNFα, and when administered after disease onset, allows eroded joints to heal.

12.2 Pharmacodynamics

Elevated concentrations of TNFα have been found in involved tissues and fluids of patients with RA, CD, UC, AS, PsA, and Ps. In RA, treatment with Infliximab reduced infiltration of inflammatory cells into inflamed areas of the joint as well as expression of molecules mediating cellular adhesion [E-selectin, intercellular adhesion molecule-1 (ICAM-1) and vascular cell adhesion molecule-1 (VCAM-1)], chemoattraction [IL-8 and monocyte chemotactic protein (MCP-1)] and tissue degradation [matrix metalloproteinase (MMP) 1 and 3]. In CD, treatment with Infliximab reduced infiltration of inflammatory cells and TNFα production in inflamed areas of the intestine, and reduced the proportion of mononuclear cells from the lamina propria able to express TNFα and interferon. After treatment with Infliximab, patients with RA or CD exhibited decreased levels of serum IL-6 and C-reactive protein (CRP) compared to baseline. Peripheral blood lymphocytes from Infliximab-treated patients showed no significant decrease in number or in proliferative responses to in vitromitogenic stimulation when compared to cells from untreated patients. In PsA, treatment with Infliximab resulted in a reduction in the number of T-cells and blood vessels in the synovium and psoriatic skin lesions as well as a reduction of macrophages in the synovium. In Ps, Infliximab treatment may reduce the epidermal thickness and infiltration of inflammatory cells. The relationship between these pharmacodynamic activities and the mechanism(s) by which Infliximab exerts its clinical effects is unknown.

12.3 Pharmacokinetics

In adults, single intravenous (IV) infusions of 3 mg/kg to 20 mg/kg (two times the maximum recommended dose for any indication) showed a linear relationship between the dose administered and the maximum serum concentration. The volume of distribution at steady state was independent of dose and indicated that infliximab was distributed primarily within the vascular compartment. Pharmacokinetic results for single doses of 3 mg/kg to 10 mg/kg in RA, 5 mg/kg in CD, and 3 mg/kg to 5 mg/kg in Ps indicate that the median terminal half-life of infliximab is 7.7 to 9.5 days.

Following an initial dose of Infliximab, repeated infusions at 2 and 6 weeks resulted in predictable concentration-time profiles following each treatment. No systemic accumulation of infliximab occurred upon continued repeated treatment with 3 mg/kg or 10 mg/kg at 4- or 8-week intervals. Development of antibodies to infliximab increased infliximab clearance. At 8 weeks after a maintenance dose of 3 to 10 mg/kg of Infliximab, median infliximab serum concentrations ranged from approximately 0.5 to 6 mcg/mL; however, infliximab concentrations were not detectable (<0.1 mcg/mL) in patients who became positive for antibodies to infliximab. No major differences in clearance or volume of distribution were observed in patient subgroups defined by age, weight, or gender. It is not known if there are differences in clearance or volume of distribution in patients with marked impairment of hepatic or renal function.

Infliximab pharmacokinetic characteristics (including peak and trough concentrations and terminal half-life) were similar in pediatric (aged 6 to 17 years) and adult patients with CD or UC following the administration of 5 mg/kg of Infliximab.

13 NONCLINICAL TOXICOLOGY

13.1 Carcinogenesis, Mutagenesis, Impairment of Fertility

A 6-month study in CD-1 mice was conducted to assess the tumorigenic potential of cV1q anti-mouse TNFα, an analogous antibody. No evidence of tumorigenicity was observed in mice that received intravenous doses of 10 mg/kg or 40 mg/kg cV1q given weekly. The relevance of this study for human risk is unknown. No impairment of fertility or reproductive performance indices were observed in male or female mice that received cV1q, an analogous mouse antibody, at intravenous doses up to 40 mg/kg given weekly.

14 CLINICAL STUDIES

14.1 Adult Crohn's Disease

Active Crohn's Disease in Adults

The safety and efficacy of single and multiple doses of Infliximab were assessed in 2 randomized, double-blind, placebo-controlled clinical studies in 653 adult patients with moderate to severely active CD [Crohn's Disease Activity Index (CDAI) ≥220 and ≤400] with an inadequate response to prior conventional therapies. Concomitant stable doses of aminosalicylates, corticosteroids and/or immunomodulatory agents were permitted and 92% of patients continued to receive at least one of these medications.

In the single-dose trial of 108 adult patients, 16% (4/25) of placebo patients achieved a clinical response (decrease in CDAI ≥70 points) at Week 4 vs. 81% (22/27) of patients receiving 5 mg/kg Infliximab (p<0.001, two-sided, Fisher's Exact test). Additionally, 4% (1/25) of placebo patients and 48% (13/27) of patients receiving 5 mg/kg Infliximab achieved clinical remission (CDAI<150) at Week 4.

In a multidose trial (ACCENT I [Study Crohn's I]), 545 adult patients received 5 mg/kg at Week 0 and were then randomized to one of three treatment groups; the placebo maintenance group received placebo at Weeks 2 and 6, and then every 8 weeks; the 5 mg/kg maintenance group received 5 mg/kg at Weeks 2 and 6, and then every 8 weeks; and the 10 mg/kg maintenance group received 5 mg/kg at Weeks 2 and 6, and then 10 mg/kg every 8 weeks. Patients in response at Week 2 were randomized and analyzed separately from those not in response at Week 2. Corticosteroid taper was permitted after Week 6.

At Week 2, 57% (311/545) of patients were in clinical response. At Week 30, a significantly greater proportion of these patients in the 5 mg/kg and 10 mg/kg maintenance groups achieved clinical remission compared to patients in the placebo maintenance group (Table 3).

Additionally, a significantly greater proportion of patients in the 5 mg/kg and 10 mg/kg Infliximab maintenance groups were in clinical remission and were able to discontinue corticosteroid use compared to patients in the placebo maintenance group at Week 54 (Table 3).

Table 3: Clinical Remission and Steroid Withdrawal in Adult Patients with CD (Study Crohn's I)
 | Single 5-mg/kg Dose [Infliximab at Week 0] | Three-Dose Induction [Infliximab 5 mg/kg administered at Weeks 0, 2 and 6]
 | Placebo Maintenance | Infliximab Maintenance q8 wks
 |  | 5 mg/kg | 10 mg/kg
Week 30 | 25/102 | 41/104 | 48/105
Clinical remission | 25% | 39% | 46%
P-value [P-values represent pairwise comparisons to placebo] |  | 0.022 | 0.001
Week 54 | 6/54 | 14/56 | 18/53
Patients in remission able to discontinue corticosteroid use [Of those receiving corticosteroids at baseline] | 11% | 25% | 34%
P-value |  | 0.059 | 0.005

Patients in the Infliximab maintenance groups (5 mg/kg and 10 mg/kg) had a longer time to loss of response than patients in the placebo maintenance group (Figure 1). At Weeks 30 and 54, significant improvement from baseline was seen among the 5 mg/kg and 10 mg/kg Infliximab-treated groups compared to the placebo group in the disease-specific inflammatory bowel disease questionnaire (IBDQ), particularly the bowel and systemic components, and in the physical component summary score of the general health-related quality of life questionnaire SF-36.

Figure 1: Kaplan-Meier Estimate of the Proportion of Adults with CD Who Had Not Lost Response Through Week 54 (Study Crohn's I)

In a subset of 78 patients who had mucosal ulceration at baseline and who participated in an endoscopic substudy, 13 of 43 patients in the Infliximab maintenance group had endoscopic evidence of mucosal healing compared to 1 of 28 patients in the placebo group at Week 10. Of the Infliximab-treated patients showing mucosal healing at Week 10, 9 of 12 patients also showed mucosal healing at Week 54.

Patients who achieved a response and subsequently lost response were eligible to receive Infliximab on an episodic basis at a dose that was 5 mg/kg higher than the dose to which they were randomized. The majority of such patients responded to the higher dose. Among patients who were not in response at Week 2, 59% (92/157) of Infliximab maintenance patients responded by Week 14 compared to 51% (39/77) of placebo maintenance patients. Among patients who did not respond by Week 14, additional therapy did not result in significantly more responses [see Dosage and Administration (2)] .

Fistulizing Crohn's Disease in Adults

The safety and efficacy of Infliximab were assessed in 2 randomized, double-blind, placebo-controlled studies in adult patients with fistulizing CD with fistula(s) that were of at least 3 months duration. Concurrent use of stable doses of corticosteroids, 5-aminosalicylates, antibiotics, MTX, 6-mercaptopurine (6-MP) and/or azathioprine (AZA) was permitted.

In the first trial, 94 adult patients received 3 doses of either placebo or Infliximab at Weeks 0, 2 and 6. Fistula response (≥50% reduction in number of enterocutaneous fistulas draining upon gentle compression on at least 2 consecutive visits without an increase in medication or surgery for CD) was seen in 68% (21/31) of patients in the 5 mg/kg Infliximab group (P=0.002) and 56% (18/32) of patients in the 10 mg/kg Infliximab group (P=0.021) vs. 26% (8/31) of patients in the placebo arm. The median time to onset of response and median duration of response in Infliximab-treated patients was 2 and 12 weeks, respectively. Closure of all fistulas was achieved in 52% of Infliximab-treated patients compared with 13% of placebo-treated patients (P<0.001).

In the second trial (ACCENT II [Study Crohn's II]), adult patients who were enrolled had to have at least 1 draining enterocutaneous (perianal, abdominal) fistula. All patients received 5 mg/kg Infliximab at Weeks 0, 2 and 6. Patients were randomized to placebo or 5 mg/kg Infliximab maintenance at Week 14. Patients received maintenance doses at Week 14 and then every 8 weeks through Week 46. Patients who were in fistula response (fistula response was defined the same as in the first trial) at both Weeks 10 and 14 were randomized separately from those not in response. The primary endpoint was time from randomization to loss of response among those patients who were in fistula response.

Among the randomized patients (273 of the 296 initially enrolled), 87% had perianal fistulas and 14% had abdominal fistulas. Eight percent also had rectovaginal fistulas. Greater than 90% of the patients had received previous immunosuppressive and antibiotic therapy.

At Week 14, 65% (177/273) of patients were in fistula response. Patients randomized to Infliximab maintenance had a longer time to loss of fistula response compared to the placebo maintenance group (Figure 2). At Week 54, 38% (33/87) of Infliximab-treated patients had no draining fistulas compared with 22% (20/90) of placebo-treated patients (P=0.02). Compared to placebo maintenance, patients on Infliximab maintenance had a trend toward fewer hospitalizations.

Figure 2: Life Table Estimates of the Proportion of Adult CD Patients Who Had Not Lost Fistula Response Through Week 54 (Study Crohn's II)

Patients who achieved a fistula response and subsequently lost response were eligible to receive Infliximab maintenance therapy at a dose that was 5 mg/kg higher than the dose to which they were randomized. Of the placebo maintenance patients, 66% (25/38) responded to 5 mg/kg Infliximab, and 57% (12/21) of Infliximab maintenance patients responded to 10 mg/kg.

Patients who had not achieved a response by Week 14 were unlikely to respond to additional doses of Infliximab.

Similar proportions of patients in either group developed new fistulas (17% overall) and similar numbers developed abscesses (15% overall).

14.2 Pediatric Crohn's Disease

The safety and efficacy of Infliximab were assessed in a randomized, open-label study (Study Peds Crohn's) in 112 pediatric patients aged 6 to 17 years old with moderately to severely active CD and an inadequate response to conventional therapies. The median age was 13 years and the median Pediatric Crohn's Disease Activity Index (PCDAI) was 40 (on a scale of 0 to 100). All patients were required to be on a stable dose of 6-MP, AZA, or MTX; 35% were also receiving corticosteroids at baseline.

All patients received induction dosing of 5 mg/kg Infliximab at Weeks 0, 2, and 6. At Week 10, 103 patients were randomized to a maintenance regimen of 5 mg/kg Infliximab given either every 8 weeks or every 12 weeks.

At Week 10, 88% of patients were in clinical response (defined as a decrease from baseline in the PCDAI score of ≥15 points and total PCDAI score of ≤30 points), and 59% were in clinical remission (defined as PCDAI score of ≤10 points).

The proportion of pediatric patients achieving clinical response at Week 10 compared favorably with the proportion of adults achieving a clinical response in Study Crohn's I. The study definition of clinical response in Study Peds Crohn's was based on the PCDAI score, whereas the CDAI score was used in the adult Study Crohn's I.

At both Week 30 and Week 54, the proportion of patients in clinical response was greater in the every 8-week treatment group than in the every 12-week treatment group (73% vs. 47% at Week 30, and 64% vs. 33% at Week 54). At both Week 30 and Week 54, the proportion of patients in clinical remission was also greater in the every 8-week treatment group than in the every 12-week treatment group (60% vs. 35% at Week 30, and 56% vs. 24% at Week 54), (Table 4).

For patients in Study Peds Crohn's receiving corticosteroids at baseline, the proportion of patients able to discontinue corticosteroids while in remission at Week 30 was 46% for the every 8-week maintenance group and 33% for the every 12-week maintenance group. At Week 54, the proportion of patients able to discontinue corticosteroids while in remission was 46% for the every 8-week maintenance group and 17% for the every 12-week maintenance group.

Table 4: Response and Remission in Study Peds Crohn's
 | 5 mg/kg Infliximab
 | Every 8 Week | Every 12 Week
 | Treatment Group | Treatment Group
Patients randomized | 52 | 51
Clinical Response [Defined as a decrease from baseline in the PCDAI score of ≥15 points and total score of ≤30 points.]
Week 30 | 73% [P-value <0.01] | 47%
Week 54 | 64% | 33%
Clinical Remission [Defined as a PCDAI score of ≤10 points.]
Week 30 | 60% [P-value <0.05] | 35%
Week 54 | 56% | 24%

14.3 Adult Ulcerative Colitis

The safety and efficacy of Infliximab were assessed in 2 randomized, double-blind, placebo-controlled clinical studies in 728 adult patients with moderately to severely active UC (Mayo score 6 to 12 [of possible range 0 to 12], Endoscopy subscore ≥2) with an inadequate response to conventional oral therapies (Studies UC I and UC II). Concomitant treatment with stable doses of aminosalicylates, corticosteroids and/or immunomodulatory agents was permitted. Corticosteroid taper was permitted after Week 8. Patients were randomized at week 0 to receive either placebo, 5 mg/kg Infliximab or 10 mg/kg Infliximab at Weeks 0, 2, 6, and every 8 weeks thereafter through Week 46 in Study UC I, and at Weeks 0, 2, 6, and every 8 weeks thereafter through Week 22 in Study UC II. In Study UC II, patients were allowed to continue blinded therapy to Week 46 at the investigator's discretion.

Adult patients in Study UC I had failed to respond or were intolerant to oral corticosteroids, 6-MP, or AZA. Adult patients in Study UC II had failed to respond or were intolerant to the above treatments and/or aminosalicylates. Similar proportions of patients in Studies UC I and UC II were receiving corticosteroids (61% and 51%, respectively), 6-MP/AZA (49% and 43%) and aminosalicylates (70% and 75%) at baseline. More patients in Study UC II than UC I were taking solely aminosalicylates for UC (26% vs. 11%, respectively). Clinical response was defined as a decrease from baseline in the Mayo score by ≥30% and ≥3 points, accompanied by a decrease in the rectal bleeding subscore of ≥1 or a rectal bleeding subscore of 0 or 1.

Clinical Response, Clinical Remission, and Mucosal Healing

In both Study UC I and Study UC II, greater percentages of patients in both Infliximab groups achieved clinical response, clinical remission and mucosal healing than in the placebo group. Each of these effects was maintained through the end of each trial (Week 54 in Study UC I, and Week 30 in Study UC II). In addition, a greater proportion of patients in Infliximab groups demonstrated sustained response and sustained remission than in the placebo groups (Table 5).

Of patients on corticosteroids at baseline, greater proportions of adult patients in the Infliximab treatment groups were in clinical remission and able to discontinue corticosteroids at Week 30 compared with the patients in the placebo treatment groups (22% in Infliximab treatment groups vs. 10% in placebo group in Study UC I; 23% in Infliximab treatment groups vs. 3% in placebo group in Study UC II). In Study UC I, this effect was maintained through Week 54 (21% in Infliximab treatment groups vs. 9% in placebo group). The Infliximab-associated response was generally similar in the 5 mg/kg and 10 mg/kg dose groups.

Table 5: Response, Remission and Mucosal Healing in Adult UC Studies (Studies UC I and UC II)
 | Study UC I |  |  | Study UC II
 | Placebo | 5 mg/kg Infliximab | 10 mg/kg Infliximab | Placebo | 5 mg/kg Infliximab | 10 mg/kg Infliximab
Patients randomized | 121 | 121 | 122 | 123 | 121 | 120
Clinical Response [Defined as a decrease from baseline in the Mayo score by ≥30% and ≥3 points, accompanied by a decrease in the rectal bleeding subscore of ≥1 or a rectal bleeding subscore of 0 or 1. (The Mayo score consists of the sum of four subscores: stool frequency, rectal bleeding, physician's global assessment and endoscopy findings).] , [Patients who had a prohibited change in medication, had an ostomy or colectomy, or discontinued study infusions due to lack of efficacy are considered to not be in clinical response, clinical remission or mucosal healing from the time of the event onward.]
Week 8 | 37% | 69% [P<0.001,] | 62% | 29% | 65% | 69%
Week 30 | 30% | 52% | 51% [P<0.01] | 26% | 47% | 60%
Week 54 | 20% | 45% | 44% | NA | NA | NA
Sustained Response
(Clinical response at both Weeks 8 and 30) | 23% | 49% | 46% | 15% | 41% | 53%
(Clinical response at Weeks 8, 30, and 54) | 14% | 39% | 37% | NA | NA | NA
Clinical Remission [Defined as a Mayo score ≤2 points, no individual subscore >1.] ,
Week 8 | 15% | 39% | 32% | 6% | 34% | 28%
Week 30 | 16% | 34% | 37% | 11% | 26% | 36%
Week 54 | 17% | 35% | 34% | NA | NA | NA
Sustained Remission
(Clinical remission at both Weeks 8 and 30) | 8% | 23% | 26% | 2% | 15% | 23%
(Clinical remission at Weeks 8, 30 and 54) | 7% | 20% | 20% | NA | NA | NA
Mucosal Healing [Defined as a 0 or 1 on the endoscopy subscore of the Mayo score.] ,
Week 8 | 34% | 62% | 59% | 31% | 60% | 62%
Week 30 | 25% | 50% | 49% | 30% | 46% | 57%
Week 54 | 18% | 45% | 47% | NA | NA | NA

The improvement with Infliximab was consistent across all Mayo subscores through Week 54 (Study UC I shown in Table 6; Study UC II through Week 30 was similar).

Table 6: Proportion of Adult UC Patients in Study UC I with Mayo Subscores Indicating Inactive or Mild Disease Through Week 54
 | Study UC I
 |  | Infliximab
 | Placebo | 5 mg/kg | 10 mg/kg
 | (n=121) | (n=121) | (n=122)
Stool frequency
Baseline | 17% | 17% | 10%
Week 8 | 35% | 60% | 58%
Week 30 | 35% | 51% | 53%
Week 54 | 31% | 52% | 51%
Rectal bleeding
Baseline | 54% | 40% | 48%
Week 8 | 74% | 86% | 80%
Week 30 | 65% | 74% | 71%
Week 54 | 62% | 69% | 67%
Physician's Global Assessment
Baseline | 4% | 6% | 3%
Week 8 | 44% | 74% | 64%
Week 30 | 36% | 57% | 55%
Week 54 | 26% | 53% | 53%
Endoscopy findings
Baseline | 0% | 0% | 0%
Week 8 | 34% | 62% | 59%
Week 30 | 26% | 51% | 52%
Week 54 | 21% | 50% | 51%

14.4 Pediatric Ulcerative Colitis

The safety and effectiveness of Infliximab for reducing signs and symptoms and inducing and maintaining clinical remission in pediatric patients aged 6 years and older with moderately to severely active UC who have had an inadequate response to conventional therapy are supported by evidence from adequate and well-controlled studies of Infliximab in adults. Additional safety and pharmacokinetic data were collected in an open-label pediatric UC trial in 60 pediatric patients aged 6 through 17 years (median age 14.5 years) with moderately to severely active UC (Mayo score of 6 to 12; Endoscopic subscore ≥2) and an inadequate response to conventional therapies. At baseline, the median Mayo score was 8, 53% of patients were receiving immunomodulator therapy (6-MP/AZA/MTX), and 62% of patients were receiving corticosteroids (median dose 0.5 mg/kg/day in prednisone equivalents). Discontinuation of immunomodulators and corticosteroid taper were permitted after Week 0.

All patients received induction dosing of 5 mg/kg Infliximab at Weeks 0, 2, and 6. Patients who did not respond to Infliximab at Week 8 received no further Infliximab and returned for safety follow-up. At Week 8, 45 patients were randomized to a maintenance regimen of 5 mg/kg Infliximab given either every 8 weeks through Week 46 or every 12 weeks through Week 42. Patients were allowed to change to a higher dose and/or more frequent administration schedule if they experienced loss of response.

Clinical response at Week 8 was defined as a decrease from baseline in the Mayo score by ≥30% and ≥3 points, including a decrease in the rectal bleeding subscore by ≥1 points or achievement of a rectal bleeding subscore of 0 or 1.

Clinical remission at Week 8 was measured by the Mayo score, defined as a Mayo score of ≤2 points with no individual subscore >1. Clinical remission was also assessed at Week 8 and Week 54 using the Pediatric Ulcerative Colitis Activity Index (PUCAI)^1score and was defined by a PUCAI score of <10 points.

Endoscopies were performed at baseline and at Week 8. A Mayo endoscopy subscore of 0 indicated normal or inactive disease and a subscore of 1 indicated mild disease (erythema, decreased vascular pattern, or mild friability).

Of the 60 patients treated, 44 were in clinical response at Week 8. Of 32 patients taking concomitant immunomodulators at baseline, 23 achieved clinical response at Week 8, compared to 21 of 28 of those not taking concomitant immunomodulators at baseline. At Week 8, 24 of 60 patients were in clinical remission as measured by the Mayo score and 17 of 51 patients were in remission as measured by the PUCAI score.

At Week 54, 8 of 21 patients in the every 8-week maintenance group and 4 of 22 patients in the every 12-week maintenance group achieved remission as measured by the PUCAI score.

During maintenance phase, 23 of 45 randomized patients (9 in the every 8-week group and 14 in the every 12-week group) required an increase in their dose and/or increase in frequency of Infliximab administration due to loss of response. Nine of the 23 patients who required a change in dose had achieved remission at Week 54. Seven of those patients received the 10 mg/kg every 8-week dosing.

14.5 Rheumatoid Arthritis

The safety and efficacy of Infliximab in adult patients with RA were assessed in 2 multicenter, randomized, double-blind, pivotal trials: ATTRACT (Study RA I) and ASPIRE (Study RA II). Concurrent use of stable doses of folic acid, oral corticosteroids (≤10 mg/day) and/or non-steroidal anti-inflammatory drugs (NSAIDs) was permitted.

Study RA I was a placebo-controlled study of 428 patients with active RA despite treatment with MTX. Patients enrolled had a median age of 54 years, median disease duration of 8.4 years, median swollen and tender joint count of 20 and 31 respectively, and were on a median dose of 15 mg/wk of MTX. Patients received either placebo+MTX or one of 4 doses/schedules of Infliximab+MTX: 3 mg/kg or 10 mg/kg of Infliximab by IV infusion at Weeks 0, 2 and 6 followed by additional infusions every 4 or 8 weeks in combination with MTX.

Study RA II was a placebo-controlled study of 3 active treatment arms in 1004 MTX naive patients of 3 or fewer years' duration active RA. Patients enrolled had a median age of 51 years with a median disease duration of 0.6 years, median swollen and tender joint count of 19 and 31 , respectively, and >80% of patients had baseline joint erosions. At randomization, all patients received MTX (optimized to 20 mg/wk by Week 8) and either placebo, 3 mg/kg or 6 mg/kg Infliximab at Weeks 0, 2, and 6 and every 8 weeks thereafter.

Data on use of Infliximab without concurrent MTX are limited [see Adverse Reactions (6.1)] .

Clinical Response

In Study RA I, all doses/schedules of Infliximab+MTX resulted in improvement in signs and symptoms as measured by the American College of Rheumatology response criteria (ACR 20) with a higher percentage of patients achieving an ACR 20, 50 and 70 compared to placebo+MTX (Table 7). This improvement was observed at Week 2 and maintained through Week 102. Greater effects on each component of the ACR 20 were observed in all patients treated with Infliximab+MTX compared to placebo+MTX (Table 8). More patients treated with Infliximab reached a major clinical response than placebo-treated patients (Table 7).

In Study RA II, after 54 weeks of treatment, both doses of Infliximab+MTX resulted in statistically significantly greater response in signs and symptoms compared to MTX alone as measured by the proportion of patients achieving ACR 20, 50 and 70 responses (Table 7). More patients treated with Infliximab reached a major clinical response than placebo-treated patients (Table 7).

Table 7: ACR Response (percent of patients) in Adult RA Patients (Studies RA I and RA II)
 | Study RA I |  |  |  |  | Study RA II
 |  | Infliximab+MTX |  |  |  |  | Infliximab+MTX
 |  | 3 mg/kg |  | 10 mg/kg |  |  | 3 mg/kg | 6 mg/kg
Response | Placebo+MTX | q8 wks | q4 wks | q8 wks | q4 wks | Placebo+MTX | q8 wks | q8 wks
 | (n=88) | (n=86) | (n=86) | (n=87) | (n=81) | (n=274) | (n=351) | (n=355)
ACR 20
Week 30 | 20% | 50% [P≤0.001] | 50% | 52% | 58% | N/A | N/A | N/A
Week 54 | 17% | 42% | 48% | 59% | 59% | 54% | 62% [P<0.05] | 66%
ACR 50
Week 30 | 5% | 27% | 29% | 31% | 26% | N/A | N/A | N/A
Week 54 | 9% | 21% | 34% | 40% | 38% | 32% | 46% | 50%
ACR 70
Week 30 | 0% | 8% [P<0.01] | 11% | 18% | 11% | N/A | N/A | N/A
Week 54 | 2% | 11% | 18% | 26% | 19% | 21% | 33% | 37%
Major clinical response [A major clinical response was defined as a 70% ACR response for 6 consecutive months (consecutive visits spanning at least 26 weeks) through Week 102 for Study RA I and Week 54 for Study RA II.] | 0% | 7% | 8% | 15% | 6% | 8% | 12% | 17%

Table 8: Components of ACR 20 at Baseline and 54 Weeks (Study RA I)
 | Placebo+MTX |  | Infliximab+MTX [All doses/schedules of Infliximab+MTX]
Parameter (medians) | (n=88) |  | (n=340)
 | Baseline | Week 54 | Baseline | Week 54
No. of Tender Joints | 24 | 16 | 32 | 8
No. of Swollen Joints | 19 | 13 | 20 | 7
Pain [Visual Analog Scale (0=best, 10=worst)] | 6.7 | 6.1 | 6.8 | 3.3
Physician's Global Assessment | 6.5 | 5.2 | 6.2 | 2.1
Patient's Global Assessment | 6.2 | 6.2 | 6.3 | 3.2
Disability Index (HAQ-DI) [Health Assessment Questionnaire, measurement of 8 categories: dressing and grooming, arising, eating, walking, hygiene, reach, grip, and activities (0=best, 3=worst)] | 1.8 | 1.5 | 1.8 | 1.3
CRP (mg/dL) | 3.0 | 2.3 | 2.4 | 0.6

Radiographic Response

Structural damage in both hands and feet was assessed radiographically at Week 54 by the change from baseline in the van der Heijde-modified Sharp (vdH-S) score, a composite score of structural damage that measures the number and size of joint erosions and the degree of joint space narrowing in hands/wrists and feet.

In Study RA I, approximately 80% of patients had paired X-ray data at 54 weeks and approximately 70% at 102 weeks. The inhibition of progression of structural damage was observed at 54 weeks (Table 9) and maintained through 102 weeks.

In Study RA II, >90% of patients had at least 2 evaluable X-rays. Inhibition of progression of structural damage was observed at Weeks 30 and 54 (Table 9) in the Infliximab+MTX groups compared to MTX alone. Patients treated with Infliximab+MTX demonstrated less progression of structural damage compared to MTX alone, whether baseline acute-phase reactants (ESR and CRP) were normal or elevated: patients with elevated baseline acute-phase reactants treated with MTX alone demonstrated a mean progression in vdH-S score of 4.2 units compared to patients treated with Infliximab+MTX who demonstrated 0.5 units of progression; patients with normal baseline acute phase reactants treated with MTX alone demonstrated a mean progression in vdH-S score of 1.8 units compared to Infliximab+MTX who demonstrated 0.2 units of progression. Of patients receiving Infliximab+MTX, 59% had no progression (vdH-S score ≤0 unit) of structural damage compared to 45% of patients receiving MTX alone. In a subset of patients who began the study without erosions, Infliximab+MTX maintained an erosion-free state at 1 year in a greater proportion of patients than MTX alone, 79% (77/98) vs. 58% (23/40), respectively (P<0.01). Fewer patients in the Infliximab+MTX groups (47%) developed erosions in uninvolved joints compared to MTX alone (59%).

Table 9: Radiographic Change from Baseline to Week 54 in Adult RA Patients (Studies RA I and RA II)
 | Study RA I |  |  | Study RA II
 |  | Infliximab+MTX |  |  | Infliximab+MTX
 |  | 3 mg/kg | 10 mg/kg |  | 3 mg/kg | 6 mg/kg
 | Placebo+MTX | q8 wks | q8 wks | Placebo+MTX | q8 wks | q8 wks
 | (n=64) | (n=71) | (n=77) | (n=282) | (n=359) | (n=363)
Total Score
Baseline
Mean | 79 | 78 | 65 | 11.3 | 11.6 | 11.2
Median | 55 | 57 | 56 | 5.1 | 5.2 | 5.3
Change from baseline
Mean | 6.9 | 1.3 [P<0.001 for each outcome against placebo.] | 0.2 | 3.7 | 0.4 | 0.5
Median | 4.0 | 0.5 | 0.5 | 0.4 | 0.0 | 0.0
Erosion Score
Baseline
Mean | 44 | 44 | 33 | 8.3 | 8.8 | 8.3
Median | 25 | 29 | 22 | 3.0 | 3.8 | 3.8
Change from baseline
Mean | 4.1 | 0.2 | 0.2 | 3.0 | 0.3 | 0.1
Median | 2.0 | 0.0 | 0.5 | 0.3 | 0.0 | 0.0
JSN Score
Baseline
Mean | 36 | 34 | 31 | 3.0 | 2.9 | 2.9
Median | 26 | 29 | 24 | 1.0 | 1.0 | 1.0
Change from baseline
Mean | 2.9 | 1.1 | 0.0 | 0.6 | 0.1 | 0.2
Median | 1.5 | 0.0 | 0.0 | 0.0 | 0.0 | 0.0

Physical Function Response

Physical function and disability were assessed using the Health Assessment Questionnaire (HAQ-DI) and the general health-related quality of life questionnaire SF-36.

In Study RA I, all doses/schedules of Infliximab+MTX showed significantly greater improvement from baseline in HAQ-DI and SF-36 physical component summary score averaged over time through Week 54 compared to placebo+MTX, and no worsening in the SF-36 mental component summary score. The median (interquartile range) improvement from baseline to Week 54 in HAQ-DI was 0.1 (-0.1, 0.5) for the placebo+MTX group and 0.4 (0.1, 0.9) for Infliximab+MTX (p<0.001). Both HAQ-DI and SF-36 effects were maintained through Week 102. Approximately 80% of patients in all doses/schedules of Infliximab+MTX remained in the trial through 102 weeks.

In Study RA II, both Infliximab treatment groups showed greater improvement in HAQ-DI from baseline averaged over time through Week 54 compared to MTX alone; 0.7 for Infliximab+MTX vs. 0.6 for MTX alone (P≤0.001). No worsening in the SF-36 mental component summary score was observed.

14.6 Ankylosing Spondylitis

The safety and efficacy of Infliximab were assessed in a randomized, multicenter, double-blind, placebo-controlled study in 279 adult patients with active AS. Patients were between 18 and 74 years of age, and had AS, as defined by the modified New York criteria for Ankylosing Spondylitis. Patients were to have had active disease as evidenced by both a Bath Ankylosing Spondylitis Disease Activity Index (BASDAI) score >4 (possible range 0–10) and spinal pain >4 (on a Visual Analog Scale [VAS] of 0–10). Patients with complete ankylosis of the spine were excluded from study participation, and the use of Disease Modifying Anti-Rheumatic Drugs (DMARDs) and systemic corticosteroids were prohibited. Doses of Infliximab 5 mg/kg or placebo were administered intravenously at Weeks 0, 2, 6, 12 and 18.

At 24 weeks, improvement in the signs and symptoms of AS, as measured by the proportion of patients achieving a 20% improvement in ASAS response criteria (ASAS 20), was seen in 60% of patients in the Infliximab-treated group vs. 18% of patients in the placebo group (p<0.001). Improvement was observed at Week 2 and maintained through Week 24 (Figure 3 and Table 10).

Figure 3: Proportion of Adult AS Patients Who Achieved a ASAS 20 Response

At 24 weeks, the proportions of patients achieving a 50% and a 70% improvement in the signs and symptoms of AS, as measured by ASAS response criteria (ASAS 50 and ASAS 70, respectively), were 44% and 28%, respectively, for patients receiving Infliximab, compared to 9% and 4%, respectively, for patients receiving placebo (P<0.001, Infliximab vs. placebo). A low level of disease activity (defined as a value <20 [on a scale of 0–100 mm] in each of the 4 ASAS response parameters) was achieved in 22% of Infliximab-treated patients vs. 1% in placebo-treated patients (P<0.001).

Table 10: Components of AS Disease Activity
 | Placebo (n=78) |  | Infliximab 5 mg/kg (n=201)
 | Baseline | 24 Weeks | Baseline | 24 Weeks | P-value
ASAS 20 response
Criteria (Mean)
Patient Global Assessment [Measured on a VAS with 0="none" and 10="severe"] | 6.6 | 6.0 | 6.8 | 3.8 | <0.001
Spinal pain | 7.3 | 6.5 | 7.6 | 4.0 | <0.001
BASFI [Bath Ankylosing Spondylitis Functional Index (BASFI), average of 10 questions] | 5.8 | 5.6 | 5.7 | 3.6 | <0.001
Inflammation [Inflammation, average of last 2 questions on the 6-question BASDAI] | 6.9 | 5.8 | 6.9 | 3.4 | <0.001
Acute Phase Reactants
Median CRP [CRP normal range 0–1.0 mg/dL] (mg/dL) | 1.7 | 1.5 | 1.5 | 0.4 | <0.001
Spinal Mobility (cm, Mean)
Modified Schober's test [Spinal mobility normal values: modified Schober's test: >4 cm; chest expansion:>6 cm; tragus to wall: <15 cm; lateral spinal flexion: >10 cm] | 4.0 | 5.0 | 4.3 | 4.4 | 0.75
Chest expansion | 3.6 | 3.7 | 3.3 | 3.9 | 0.04
Tragus to wall | 17.3 | 17.4 | 16.9 | 15.7 | 0.02
Lateral spinal flexion | 10.6 | 11.0 | 11.4 | 12.9 | 0.03

The median improvement from baseline in the general health-related quality-of-life questionnaire SF-36 physical component summary score at Week 24 was 10.2 for the Infliximab group vs. 0.8 for the placebo group (P<0.001). There was no change in the SF-36 mental component summary score in either the Infliximab group or the placebo group.

Results of this study were similar to those seen in a multicenter double-blind, placebo-controlled study of 70 patients with AS.

14.7 Psoriatic Arthritis

Safety and efficacy of Infliximab were assessed in a multicenter, double-blind, placebo-controlled study in 200 adult patients with active PsA despite DMARD or NSAID therapy (≥5 swollen joints and ≥5 tender joints) with 1 or more of the following subtypes: arthritis involving DIP joints (n=49), arthritis mutilans (n=3), asymmetric peripheral arthritis (n=40), polyarticular arthritis (n=100), and spondylitis with peripheral arthritis (n=8). Patients also had Ps with a qualifying target lesion ≥2 cm in diameter. Forty-six percent of patients continued on stable doses of methotrexate (≤25 mg/week). During the 24-week double-blind phase, patients received either 5 mg/kg Infliximab or placebo at Weeks 0, 2, 6, 14, and 22 (100 patients in each group). At Week 16, placebo patients with <10% improvement from baseline in both swollen and tender joint counts were switched to Infliximab induction (early escape). At Week 24, all placebo-treated patients crossed over to Infliximab induction. Dosing continued for all patients through Week 46.

Clinical Response

Treatment with Infliximab resulted in improvement in signs and symptoms, as assessed by the ACR criteria, with 58% of Infliximab-treated patients achieving ACR 20 at Week 14, compared with 11% of placebo-treated patients (P<0.001). The response was similar regardless of concomitant use of methotrexate. Improvement was observed as early as Week 2. At 6 months, the ACR 20/50/70 responses were achieved by 54%, 41%, and 27%, respectively, of patients receiving Infliximab compared to 16%, 4%, and 2%, respectively, of patients receiving placebo. Similar responses were seen in patients with each of the subtypes of PsA, although few patients were enrolled with the arthritis mutilans and spondylitis with peripheral arthritis subtypes.

Compared to placebo, treatment with Infliximab resulted in improvements in the components of the ACR response criteria, as well as in dactylitis and enthesopathy (Table 11). The clinical response was maintained through Week 54. Similar ACR responses were observed in an earlier randomized, placebo-controlled study of 104 PsA patients, and the responses were maintained through 98 weeks in an open-label extension phase.

Table 11: Components of ACR 20 and Percentage of Adult PsA Patients with 1 or More Joints with Dactylitis and Percentage of Adult PsA Patients with Enthesopathy at Baseline and Week 24
 | Placebo |  | Infliximab 5 mg/kg [P<0.001 for percent change from baseline in all components of ACR 20 at Week 24, P<0.05 for % of patients with dactylitis, and P=0.004 for % of patients with enthesopathy at Week 24]
Patients Randomized | (n=100) |  | (n=100)
 | Baseline | Week 24 | Baseline | Week 24
Parameter (medians)
No. of Tender Joints [Scale 0–68] | 24 | 20 | 20 | 6
No. of Swollen Joints [Scale 0–66] | 12 | 9 | 12 | 3
Pain [Visual Analog Scale (0=best, 10=worst)] | 6.4 | 5.6 | 5.9 | 2.6
Physician's Global Assessment | 6.0 | 4.5 | 5.6 | 1.5
Patient's Global Assessment | 6.1 | 5.0 | 5.9 | 2.5
Disability Index (HAQ-DI) [Health Assessment Questionnaire, measurement of 8 categories: dressing and grooming, arising, eating, walking, hygiene, reach, grip, and activities (0=best, 3=worst)] | 1.1 | 1.1 | 1.1 | 0.5
CRP (mg/dL) [Normal range 0–0.6 mg/dL] | 1.2 | 0.9 | 1.0 | 0.4
% Patients with 1 or more digits with dactylitis | 41 | 33 | 40 | 15
% Patients with enthesopathy | 35 | 36 | 42 | 22

Improvement in Psoriasis Area and Severity Index (PASI) in PsA patients with baseline body surface area (BSA) ≥3% (n=87 placebo, n=83 Infliximab) was achieved at Week 14, regardless of concomitant methotrexate use, with 64% of Infliximab-treated patients achieving at least 75% improvement from baseline vs. 2% of placebo-treated patients; improvement was observed in some patients as early as Week 2. At 6 months, the PASI 75 and PASI 90 responses were achieved by 60% and 39%, respectively, of patients receiving Infliximab compared to 1% and 0%, respectively, of patients receiving placebo. The PASI response was generally maintained through Week 54. [see Clinical Studies (14.8)] .

Radiographic Response

Structural damage in both hands and feet was assessed radiographically by the change from baseline in the van der Heijde-Sharp (vdH-S) score, modified by the addition of hand DIP joints. The total modified vdH-S score is a composite score of structural damage that measures the number and size of joint erosions and the degree of joint space narrowing (JSN) in the hands and feet. At Week 24, Infliximab-treated patients had less radiographic progression than placebo-treated patients (mean change of -0.70 vs. 0.82, P<0.001). Infliximab-treated patients also had less progression in their erosion scores (-0.56 vs 0.51) and JSN scores (-0.14 vs 0.31). The patients in the Infliximab group demonstrated continued inhibition of structural damage at Week 54. Most patients showed little or no change in the vdH-S score during this 12-month study (median change of 0 in both patients who initially received Infliximab or placebo). More patients in the placebo group (12%) had readily apparent radiographic progression compared with the Infliximab group (3%).

Physical Function

Physical function status was assessed using the HAQ Disability Index (HAQ-DI) and the SF-36 Health Survey. Infliximab-treated patients demonstrated significant improvement in physical function as assessed by HAQ-DI (median percent improvement in HAQ-DI score from baseline to Week 14 and 24 of 43% for Infliximab-treated patients vs 0% for placebo-treated patients).

During the placebo-controlled portion of the trial (24 weeks), 54% of Infliximab-treated patients achieved a clinically meaningful improvement in HAQ-DI (≥0.3 unit decrease) compared to 22% of placebo-treated patients. Infliximab-treated patients also demonstrated greater improvement in the SF-36 physical and mental component summary scores than placebo-treated patients. The responses were maintained for up to 2 years in an open-label extension study.

14.8 Plaque Psoriasis

The safety and efficacy of Infliximab were assessed in 3 randomized, double-blind, placebo-controlled studies in patients 18 years of age and older with chronic, stable Ps involving ≥10% BSA, a minimum PASI score of 12, and who were candidates for systemic therapy or phototherapy. Patients with guttate, pustular, or erythrodermic psoriasis were excluded from these studies. No concomitant anti-psoriatic therapies were allowed during the study, with the exception of low-potency topical corticosteroids on the face and groin after Week 10 of study initiation.

Study I (EXPRESS) evaluated 378 patients who received placebo or Infliximab at a dose of 5 mg/kg at Weeks 0, 2, and 6 (induction therapy), followed by maintenance therapy every 8 weeks. At Week 24, the placebo group crossed over to Infliximab induction therapy (5 mg/kg), followed by maintenance therapy every 8 weeks. Patients originally randomized to Infliximab continued to receive Infliximab 5 mg/kg every 8 weeks through Week 46. Across all treatment groups, the median baseline PASI score was 21 and the baseline Static Physician Global Assessment (sPGA) score ranged from moderate (52% of patients) to marked (36%) to severe (2%). In addition, 75% of patients had a BSA >20%. Seventy-one percent of patients previously received systemic therapy, and 82% received phototherapy.

Study II (EXPRESS II) evaluated 835 patients who received placebo or Infliximab at doses of 3 mg/kg or 5 mg/kg at Weeks 0, 2, and 6 (induction therapy). At Week 14, within each Infliximab dose group, patients were randomized to either scheduled (every 8 weeks) or as needed (PRN) maintenance treatment through Week 46. At Week 16, the placebo group crossed over to Infliximab induction therapy (5 mg/kg), followed by maintenance therapy every 8 weeks. Across all treatment groups, the median baseline PASI score was 18, and 63% of patients had a BSA >20%. Fifty-five percent of patients previously received systemic therapy, and 64% received a phototherapy.

Study III (SPIRIT) evaluated 249 patients who had previously received either psoralen plus ultraviolet A treatment (PUVA) or other systemic therapy for their psoriasis. These patients were randomized to receive either placebo or Infliximab at doses of 3 mg/kg or 5 mg/kg at Weeks 0, 2, and 6. At Week 26, patients with a sPGA score of moderate or worse (greater than or equal to 3 on a scale of 0 to 5) received an additional dose of the randomized treatment. Across all treatment groups, the median baseline PASI score was 19, and the baseline sPGA score ranged from moderate (62% of patients) to marked (22%) to severe (3%). In addition, 75% of patients had a BSA >20%. Of the enrolled patients, 114 (46%) received the Week 26 additional dose.

In Studies I, II and III, the primary endpoint was the proportion of patients who achieved a reduction in score of at least 75% from baseline at Week 10 by the PASI (PASI 75). In Study I and Study III, another evaluated outcome included the proportion of patients who achieved a score of "cleared" or "minimal" by the sPGA. The sPGA is a 6-category scale ranging from "5 = severe" to "0 = cleared" indicating the physician's overall assessment of the psoriasis severity focusing on induration, erythema, and scaling. Treatment success, defined as "cleared" or "minimal," consisted of none or minimal elevation in plaque, up to faint red coloration in erythema, and none or minimal fine scale over <5% of the plaque.

Study II also evaluated the proportion of patients who achieved a score of "clear" or "excellent" by the relative Physician's Global Assessment (rPGA). The rPGA is a 6-category scale ranging from "6 = worse" to "1 = clear" that was assessed relative to baseline. Overall lesions were graded with consideration to the percent of body involvement as well as overall induration, scaling, and erythema. Treatment success, defined as "clear" or "excellent," consisted of some residual pinkness or pigmentation to marked improvement (nearly normal skin texture; some erythema may be present). The results of these studies are presented in Table 12.

Table 12: Adult Psoriasis Studies I, II, and III, Percentage of Patients who Achieved PASI 75 and Percentage who Achieved Treatment "Success" with Physician's Global Assessment at Week 10
 | Placebo | Infliximab
 |  | 3 mg/kg | 5 mg/kg
Psoriasis Study I - patients randomized [Patients with missing data at Week 10 were considered as nonresponders.] | 77 | — | 301
PASI 75 | 2 (3%) | — | 242 (80%) [P<0.001 compared with placebo]
sPGA | 3 (4%) | — | 242 (80%)
Psoriasis Study II - patients randomized | 208 | 313 | 314
PASI 75 | 4 (2%) | 220 (70%) | 237 (75%)
rPGA | 2 (1%) | 217 (69%) | 234 (75%)
Psoriasis Study III - patients randomized [Patients with missing data at Week 10 were imputed by last observation.] | 51 | 99 | 99
PASI 75 | 3 (6%) | 71 (72%) | 87 (88%)
sPGA | 5 (10%) | 71 (72%) | 89 (90%)

In Study I, in the subgroup of patients with more extensive Ps who had previously received phototherapy, 85% of patients on 5 mg/kg Infliximab achieved a PASI 75 at Week 10 compared with 4% of patients on placebo.

In Study II, in the subgroup of patients with more extensive Ps who had previously received phototherapy, 72% and 77% of patients on 3 mg/kg and 5 mg/kg Infliximab achieved a PASI 75 at Week 10 respectively compared with 1% on placebo. In Study II, among patients with more extensive Ps who had failed or were intolerant to phototherapy, 70% and 78% of patients on 3 mg/kg and 5 mg/kg Infliximab achieved a PASI 75 at Week 10 respectively, compared with 2% on placebo.

Maintenance of response was studied in a subset of 292 and 297 Infliximab-treated patients in the 3 mg/kg and 5 mg/kg groups; respectively, in Study II. Stratified by PASI response at Week 10 and investigational site, patients in the active treatment groups were re-randomized to either a scheduled or as needed maintenance (PRN) therapy, beginning on Week 14.

The groups that received a maintenance dose every 8 weeks appear to have a greater percentage of patients maintaining a PASI 75 through Week 50 as compared to patients who received the as-needed or PRN doses, and the best response was maintained with the 5 mg/kg every 8-week dose. These results are shown in Figure 4. At Week 46, when Infliximab serum concentrations were at trough level, in the every 8-week dose group, 54% of patients in the 5 mg/kg group compared to 36% in the 3 mg/kg group achieved PASI 75. The lower percentage of PASI 75 responders in the 3 mg/kg every 8-week dose group compared to the 5 mg/kg group was associated with a lower percentage of patients with detectable trough serum infliximab levels. This may be related in part to higher antibody rates [see Adverse Reactions (6.1)] . In addition, in a subset of patients who had achieved a response at Week 10, maintenance of response appears to be greater in patients who received Infliximab every 8 weeks at the 5 mg/kg dose. Regardless of whether the maintenance doses are PRN or every 8 weeks, there is a decline in response in a subpopulation of patients in each group over time. The results of Study I through Week 50 in the 5 mg/kg every 8 weeks maintenance dose group were similar to the results from Study II.

Figure 4: Proportion of Adult Ps Patients Who Achieved ≥75% Improvement in PASI from Baseline through Week 50 (patients randomized at Week 14)

Efficacy and safety of Infliximab treatment beyond 50 weeks have not been evaluated in patients with Ps.

15 REFERENCES

1. Turner D, Otley AR, Mack D, et al. Development, validation, and evaluation of a pediatric ulcerative colitis activity index: A prospective multicenter study. Gastroenterology. 2007;133:423–432.

16 HOW SUPPLIED/STORAGE AND HANDLING

How Supplied

Infliximab for injection is supplied in a carton containing one single-dose vial (NDC 57894-160-01).

Each single-dose vial contains 100 mg of infliximab as a sterile, preservative-free, white lyophilized powder for reconstitution and dilution (more than one vial may be needed for a full dose) [see Dosage and Administration (2.11)].

Storage and Handling

Store unopened Infliximab vials in a refrigerator at 2 °C to 8 °C (36 °F to 46 °F).

If needed, unopened Infliximab vials may be stored at room temperatures up to a maximum of 30 °C (86 °F) for a single period of up to 6 months but not exceeding the original expiration date. The new expiration date must be written in the space provided on the carton. Once removed from the refrigerator, Infliximab cannot be returned to the refrigerator.

For storage conditions of the reconstituted and diluted product for administration, see Dosage and Administration (2.11).

17 PATIENT COUNSELING INFORMATION

Advise the patient or their caregiver to read the FDA-approved patient labeling (Medication Guide).

Patients or their caregivers should be advised of the potential benefits and risks of Infliximab. Healthcare providers should instruct their patients or their caregivers to read the Medication Guide before starting Infliximab therapy and to reread it each time they receive an infusion.

Infections

Inform patients that Infliximab increases the risk for developing serious infections. Instruct patients of the importance of contacting their healthcare provider if they develop any symptoms of an infection, including tuberculosis, invasive fungal infections, and reactivation of hepatitis B virus infections [see Warnings and Precautions (5.1, 5.3)] .

Malignancies

Malignancies have been reported among children, adolescents and young adults who received treatment with TNF blockers. Patients should be counseled about the risk of lymphoma and other malignancies while receiving Infliximab [see Warnings and Precautions (5.2)] .

Hepatotoxicity

Instruct patients to seek medical attention if they develop signs or symptoms of hepatotoxicity (e.g., jaundice) [see Warnings and Precautions (5.4)].

Heart Failure

Instruct patients to seek medical attention and consult their prescriber if they develop signs or symptoms of heart failure [see Contraindications (4)and Warnings and Precautions (5.5)] .

Hematologic Reactions

Instruct patients to seek immediate medical attention if they develop signs and symptoms suggestive of blood dyscrasias or infection (e.g., persistent fever) while on Infliximab [see Warnings and Precautions (5.6)] .

Hypersensitivity

Advise patients to seek immediate medical attention if they experience any symptoms of serious hypersensitivity reactions [see Warnings and Precautions (5.7)].

Cardiovascular and Cerebrovascular Reactions During and After Infusion

Advise patients to seek immediate medical attention if they develop any new or worsening symptoms of cardiovascular and cerebrovascular reactions which have been reported during and within 24 hours of initiation of Infliximab infusion [see Warnings and Precautions (5.8)].

Neurologic Reactions

Advise patients to seek medical attention if they develop signs or symptoms of neurologic reactions [see Warnings and Precautions (5.9)].

Live Vaccines/Therapeutic Infectious Agents

Instruct Infliximab-treated patients to avoid receiving live vaccines or therapeutic infectious agents [see Warnings and Precautions (5.13)].

Manufactured by:
Janssen Biotech, Inc.
Horsham, PA 19044

U.S. License No. 1864

MEDICATION GUIDE
Infliximab
for injection, for intravenous use

Read the Medication Guide that comes with Infliximab before you receive the first treatment, and before each time you get a treatment of Infliximab. This Medication Guide does not take the place of talking with your doctor about your medical condition or treatment.

What is the most important information I should know about Infliximab?

Infliximab may cause serious side effects, including:

1. Risk of infection

Infliximab is a medicine that affects your immune system. Infliximab can lower the ability of your immune system to fight infections. Serious infections have happened in patients receiving Infliximab. These infections include tuberculosis (TB) and infections caused by viruses, fungi or bacteria that have spread throughout the body. Some patients have died from these infections.

- Your doctor should test you for TB before starting Infliximab.
- Your doctor should monitor you closely for signs and symptoms of TB during treatment with Infliximab.

Before starting Infliximab, tell your doctor if you:

- think you have an infection. You should not start receiving Infliximab if you have any kind of infection.
- are being treated for an infection.
- have signs of an infection, such as a fever, cough, flu-like symptoms.
- have any open cuts or sores on your body.
- get a lot of infections or have infections that keep coming back.
- have diabetes or an immune system problem. People with these conditions have a higher chance for infections.
- have TB, or have been in close contact with someone with TB.
- live or have lived in certain parts of the country (such as the Ohio and Mississippi River valleys) where there is an increased risk for getting certain kinds of fungal infections (histoplasmosis, coccidioidomycosis, or blastomycosis). These infections may develop or become more severe if you receive Infliximab. If you do not know if you have lived in an area where histoplasmosis, coccidioidomycosis, or blastomycosis is common, ask your doctor.
- have or have had hepatitis B.
- use the medicines KINERET (anakinra), ORENCIA (abatacept), ACTEMRA (tocilizumab), or other medicines called biologics used to treat the same conditions as Infliximab.

After starting Infliximab, if you have an infection, any sign of an infection including a fever, cough, flu-like symptoms, or have open cuts or sores on your body, call your doctor right away. Infliximab can make you more likely to get infections or make any infection that you have worse.

2. Risk of Cancer

- There have been cases of unusual cancers in children and teenage patients using tumor necrosis factor (TNF) blocker medicines.
- For children and adults receiving TNF blocker medicines, including Infliximab, the chances of getting lymphoma or other cancers may increase.
- Some people receiving TNF blockers, including Infliximab, developed a rare type of cancer called hepatosplenic T-cell lymphoma. This type of cancer often results in death. Most of these people were male teenagers or young men. Also, most people were being treated for Crohn's disease or ulcerative colitis with a TNF blocker and another medicine called azathioprine or 6-mercaptopurine.
- People who have been treated for rheumatoid arthritis, Crohn's disease, ulcerative colitis, ankylosing spondylitis, psoriatic arthritis and plaque psoriasis for a long time may be more likely to develop lymphoma. This is especially true for people with very active disease.
- Some people treated with Infliximab have developed certain kinds of skin cancer. If any changes in the appearance of your skin or growths on your skin occur during or after your treatment with Infliximab, tell your doctor.
- Patients with Chronic Obstructive Pulmonary Disease (COPD), a specific type of lung disease, may have an increased risk for getting cancer while being treated with Infliximab.
- Some women being treated for rheumatoid arthritis with Infliximab have developed cervical cancer. For women receiving Infliximab, including those over 60 years of age, your doctor may recommend that you continue to be regularly screened for cervical cancer.
- Tell your doctor if you have ever had any type of cancer. Discuss with your doctor any need to adjust medicines you may be taking.

See the section " What are the possible side effects of Infliximab?" below for more information.

What is Infliximab?

Infliximab is a prescription medicine that is approved for patients with:

- Rheumatoid Arthritis - adults with moderately to severely active rheumatoid arthritis, along with the medicine methotrexate.
- Crohn's Disease - children 6 years and older and adults with Crohn's disease who have not responded well to other medicines.
- Ankylosing Spondylitis in adults
- Psoriatic Arthritis in adults
- Plaque Psoriasis - adult patients with plaque psoriasis that is chronic (does not go away), severe, extensive, and/or disabling.
- Ulcerative Colitis - children 6 years and older and adults with moderately to severely active ulcerative colitis who have not responded well to other medicines.

Infliximab blocks the action of a protein in your body called tumor necrosis factor-alpha (TNF-alpha). TNF-alpha is made by your body's immune system. People with certain diseases have too much TNF-alpha that can cause the immune system to attack normal healthy parts of the body. Infliximab can block the damage caused by too much TNF-alpha.

It is not known if Infliximab is safe and effective in children under 6 years of age.

Who should not receive Infliximab?

You should not receive Infliximab if you have:

- heart failure, unless your doctor has examined you and decided that you are able to receive Infliximab. Talk to your doctor about your heart failure.
- had an allergic reaction to Infliximab, or any of the other ingredients in Infliximab. See the end of this Medication Guide for a complete list of ingredients in Infliximab.

What should I tell my doctor before starting treatment with Infliximab?

Your doctor will assess your health before each treatment.

Tell your doctor about all of your medical conditions, including if you:

- have an infection (see " What is the most important information I should know about Infliximab?").
- have other liver problems including liver failure.
- have heart failure or other heart conditions. If you have heart failure, it may get worse while you receive Infliximab.
- have or have had any type of cancer.
- have had phototherapy (treatment with ultraviolet light or sunlight along with a medicine to make your skin sensitive to light) for psoriasis. You may have a higher chance of getting skin cancer while receiving Infliximab.
- have COPD, a specific type of lung disease. Patients with COPD may have an increased risk of getting cancer while receiving Infliximab.
- have or have had a condition that affects your nervous system such as:
  - multiple sclerosis, or Guillain-Barré syndrome, or
  - if you experience any numbness or tingling, or
  - if you have had a seizure.
- have recently received or are scheduled to receive a vaccine. Adults and children receiving Infliximab should not receive live vaccines (for example, the Bacille Calmette-Guérin [BCG] vaccine) or treatment with a weakened bacteria(such as BCG for bladder cancer). Adults and children should have all of their vaccines brought up to date before starting treatment with Infliximab.
- are pregnant or plan to become pregnant, are breastfeeding or plan to breastfeed. You and your doctor should decide if you should receive Infliximab while you are pregnant or breastfeeding.

If you have a baby and you were receiving Infliximab during your pregnancy, it is important to tell your baby's doctor and other health care professionals about your Infliximab use so they can decide when your baby should receive any vaccine. Certain vaccinations can cause infections.

If you received Infliximab while you were pregnant, your baby may be at higher risk for getting an infection. If your baby receives a live vaccine within 6 months after birth, your baby may develop infections with serious complications that can lead to death. This includes live vaccines such as the BCG, rotavirus, or any other live vaccines. For other types of vaccines, talk with your doctor.

How should I receive Infliximab?

- You will be given Infliximab through a needle placed in a vein (IV or intravenous infusion) in your arm.
- Your doctor may decide to give you medicine before starting the Infliximab infusion to prevent or lessen side effects.
- Only a healthcare professional should prepare the medicine and administer it to you.
- Infliximab will be given to you over a period of about 2 hours.
- If you have side effects from Infliximab, the infusion may need to be adjusted or stopped. In addition, your healthcare professional may decide to treat your symptoms.
- A healthcare professional will monitor you during the Infliximab infusion and for a period of time afterward for side effects. Your doctor may do certain tests while you are receiving Infliximab to monitor you for side effects and to see how well you respond to the treatment.
- Your doctor will determine the right dose of Infliximab for you and how often you should receive it. Make sure to discuss with your doctor when you will receive infusions and to come in for all your infusions and follow-up appointments.

What should I avoid while receiving Infliximab?

Do not take Infliximab together with medicines such as KINERET (anakinra), ORENCIA (abatacept), ACTEMRA (tocilizumab), or other medicines called biologics that are used to treat the same conditions as Infliximab.

Tell your doctor about all the medicines you take, including prescription and over-the-counter medicines, vitamins, and herbal supplements. These include any other medicines to treat Crohn's disease, ulcerative colitis, rheumatoid arthritis, ankylosing spondylitis, psoriatic arthritis or psoriasis.

Know the medicines you take. Keep a list of your medicines and show them to your doctor and pharmacist when you get a new medicine.

What are the possible side effects of Infliximab?

Infliximab can cause serious side effects, including:

See " What is the most important information I should know about Infliximab?"

Serious Infections

- Some patients, especially those 65 years and older have had serious infections while receiving Infliximab. These serious infections include TB and infections caused by viruses, fungi, or bacteria that have spread throughout the body or cause infections in certain areas (such as skin). Some patients die from these infections. If you get an infection while receiving treatment with Infliximab your doctor will treat your infection and may need to stop your Infliximab treatment.
- Tell your doctor right away if you have any of the following signs of an infection while receiving or after receiving Infliximab:

- a fever
- feel very tired
- have a cough

- have flu-like symptoms
- warm, red, or painful skin

- Your doctor will examine you for TB and perform a test to see if you have TB. If your doctor feels that you are at risk for TB, you may be treated with medicine for TB before you begin treatment with Infliximab and during treatment with Infliximab.
- Even if your TB test is negative, your doctor should carefully monitor you for TB infections while you are receiving Infliximab. Patients who had a negativeTB skin test before receiving Infliximab have developed active TB.
- If you are a chronic carrier of the hepatitis B virus, the virus can become active while you are being treated with Infliximab. In some cases, patients have died as a result of hepatitis B virus being reactivated. Your doctor should do a blood test for hepatitis B virus before you start treatment with Infliximab and occasionally while you are being treated. Tell your doctor if you have any of the following symptoms:

- feel unwell
- poor appetite

- tiredness (fatigue)
- fever, skin rash, or joint pain

Heart Failure

If you have a heart problem called congestive heart failure, your doctor should check you closely while you are receiving Infliximab. Your congestive heart failure may get worse while you are receiving Infliximab. Be sure to tell your doctor of any new or worse symptoms including:

- shortness of breath
- swelling of ankles or feet

- sudden weight gain

Treatment with Infliximab may need to be stopped if you get new or worse congestive heart failure.

Other Heart Problems

Some patients have experienced a heart attack (some of which led to death), low blood flow to the heart, or abnormal heart rhythm within 24 hours of beginning their infusion of Infliximab. Symptoms may include chest discomfort or pain, arm pain, stomach pain, shortness of breath, anxiety, lightheadedness, dizziness, fainting, sweating, nausea, vomiting, fluttering or pounding in your chest, and/or a fast or a slow heartbeat. Tell your doctor right away if you have any of these symptoms.

Liver Injury

Some patients receiving Infliximab have developed serious liver problems. Tell your doctor if you have:

- jaundice (skin and eyes turning yellow)
- dark brown-colored urine
- pain on the right side of your stomach area (right-sided abdominal pain)

- fever
- extreme tiredness (severe fatigue)

Blood Problems

In some patients receiving Infliximab, the body may not make enough of the blood cells that help fight infections or help stop bleeding. Tell your doctor if you:

- have a fever that does not go away
- bruise or bleed very easily

- look very pale

Nervous System Disorders

Some patients receiving Infliximab have developed problems with their nervous system. Tell your doctor if you have:

- changes in your vision
- numbness or tingling in any part of your body

- seizures
- weakness in your arms or legs

Some patients have experienced a stroke within approximately 24 hours of their infusion with Infliximab. Tell your doctor right away if you have symptoms of a stroke which may include: numbness or weakness of the face, arm or leg, especially on one side of the body; sudden confusion, trouble speaking or understanding; sudden trouble seeing in one or both eyes, sudden trouble walking, dizziness, loss of balance or coordination or a sudden, severe headache.

Allergic Reactions

Some patients have had allergic reactions to Infliximab. Some of these reactions were severe. These reactions can happen while you are getting your Infliximab treatment or shortly afterward. Your doctor may need to stop or pause your treatment with Infliximab and may give you medicines to treat the allergic reaction. Signs of an allergic reaction can include:

- hives (red, raised, itchy patches of skin)
- difficulty breathing
- chest pain

- high or low blood pressure
- fever
- chills

Some patients treated with Infliximab have had delayed allergic reactions. The delayed reactions occurred 3 to 12 days after receiving treatment with Infliximab. Tell your doctor right away if you have any of these signs of delayed allergic reaction to Infliximab:

- fever
- rash
- headache
- sore throat

- muscle or joint pain
- swelling of the face and hands
- difficulty swallowing

Lupus-like Syndrome

Some patients have developed symptoms that are like the symptoms of Lupus. If you develop any of the following symptoms, your doctor may decide to stop your treatment with Infliximab.

- chest discomfort or pain that does not go away
- shortness of breath

- joint pain
- rash on the cheeks or arms that gets worse in the sun

Psoriasis

Some people receiving Infliximab had new psoriasis or worsening of psoriasis they already had. Tell your doctor if you develop red scaly patches or raised bumps on the skin that are filled with pus. Your doctor may decide to stop your treatment with Infliximab.

The most common side effects of Infliximab include:

- respiratory infections, such as sinus infections and sore throat
- headache

- coughing
- stomach pain

Infusion reactions can happen up to 2 hours after your infusion of Infliximab. Symptoms of infusion reactions may include:

- fever
- chills
- chest pain

- low blood pressure or high blood pressure
- shortness of breath

- rash
- itching

Children who received Infliximab in studies for Crohn's disease showed some differences in side effects compared with adults who received Infliximab for Crohn's disease. The side effects that happened more in children were: anemia (low red blood cells), leukopenia (low white blood cells), flushing (redness or blushing), viral infections, neutropenia (low neutrophils, the white blood cells that fight infection), bone fracture, bacterial infection and allergic reactions of the breathing tract. Among patients who received Infliximab for ulcerative colitis in clinical studies, more children had infections as compared with adults.

Tell your doctor about any side effect that bothers you or does not go away.

These are not all of the side effects with Infliximab. Ask your doctor or pharmacist for more information.

Call your doctor for medical advice about side effects. You may report side effects to FDA at 1-800-FDA-1088.

General information about Infliximab

Medicines are sometimes prescribed for purposes other than those listed in a Medication Guide.

You can ask your doctor or pharmacist for information about Infliximab that is written for health professionals.

For more information call 1-800-526-7736.

What are the ingredients in Infliximab?

The active ingredient is Infliximab.

The inactive ingredients in Infliximab include: dibasic sodium phosphate dihydrate, monobasic sodium phosphate monohydrate, polysorbate 80, and sucrose. No preservatives are present.

Manufactured by: Janssen Biotech, Inc., Horsham, PA 19044
U.S. License No. 1864

This Medication Guide has been approved by the U.S. Food and Drug Administration

Revised: March 2025

PRINCIPAL DISPLAY PANEL - 100 mg Vial Box

NDC 57894-160-01

Infliximab
for injection

100 mg per vial

Attention: Dispense the enclosed
Medication Guide to each patient.

Must Reconstitute and Dilute Before
Intravenous Infusion.
Must infuse over at least 2 hours with an
in-line filter.

Rx only

Single-dose vial.
Discard unused portion.

Johnson
& Johnson